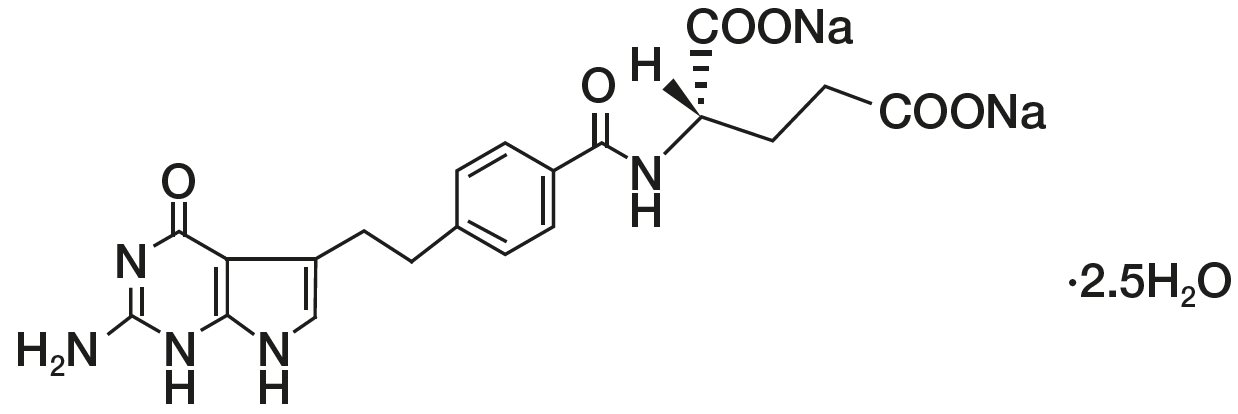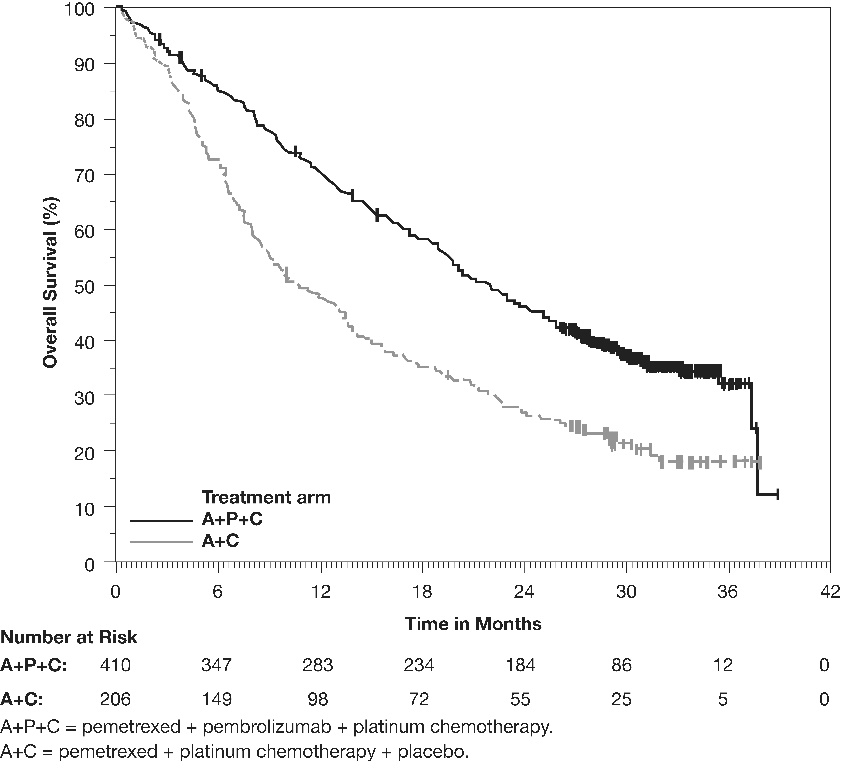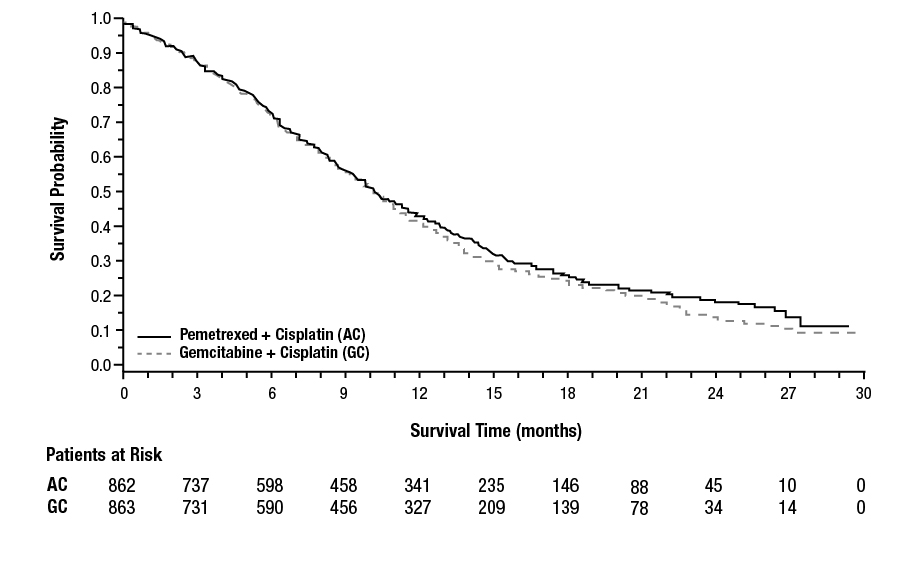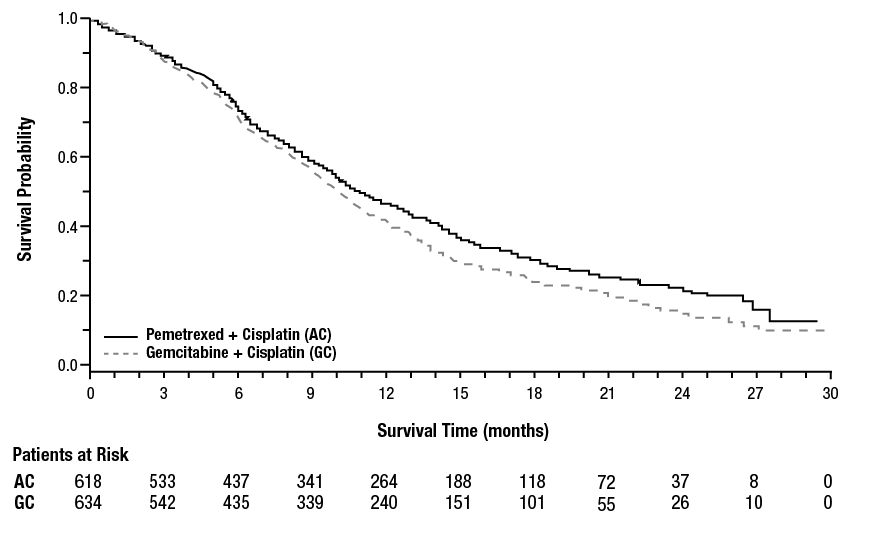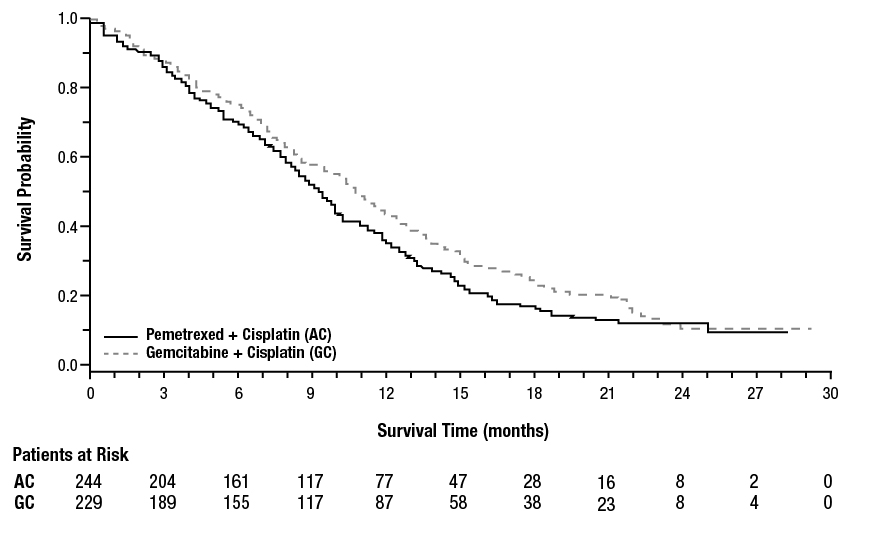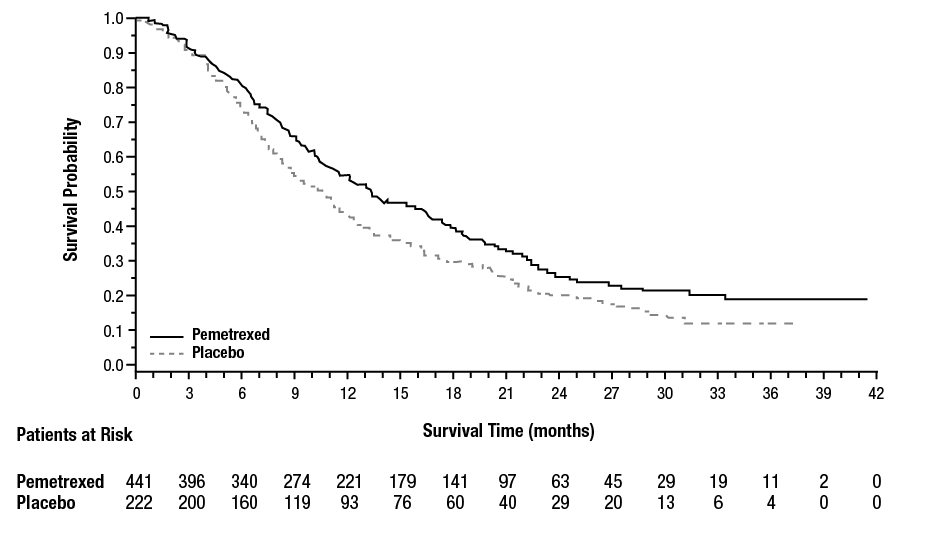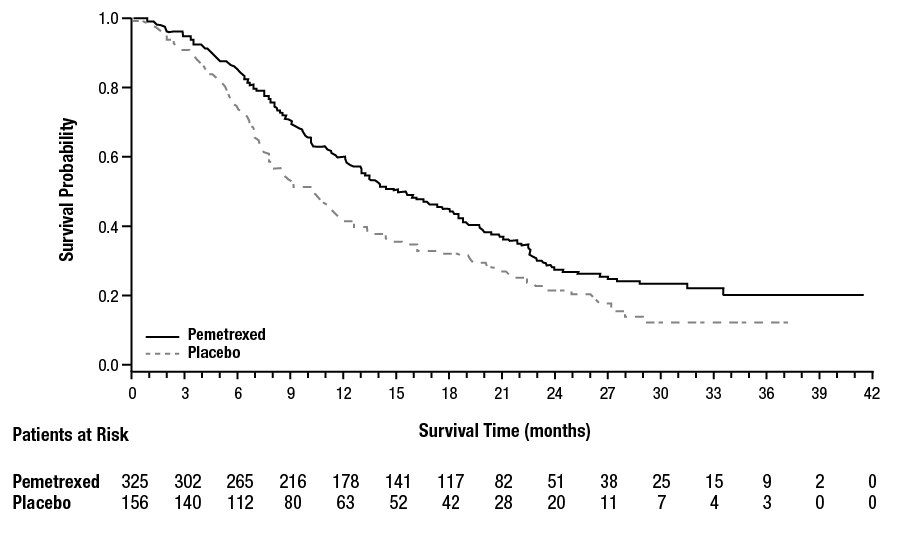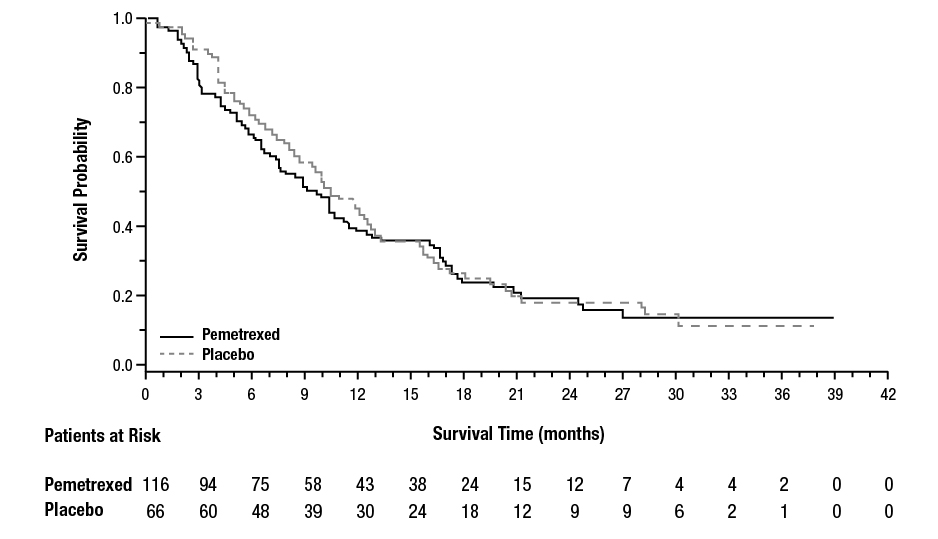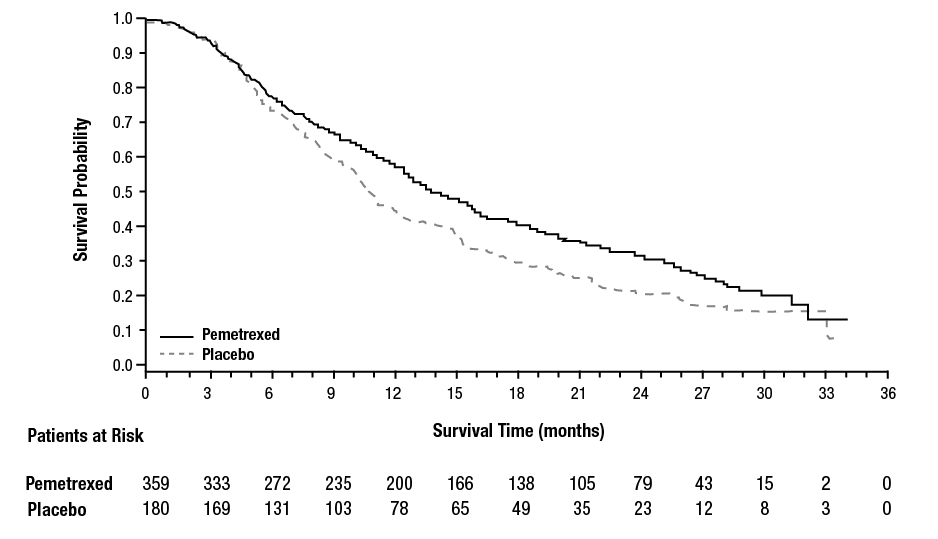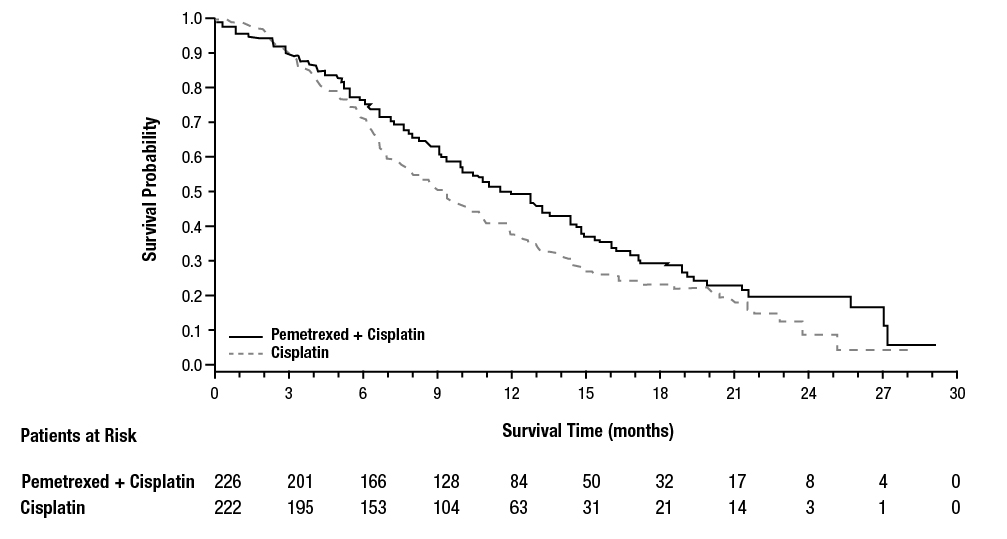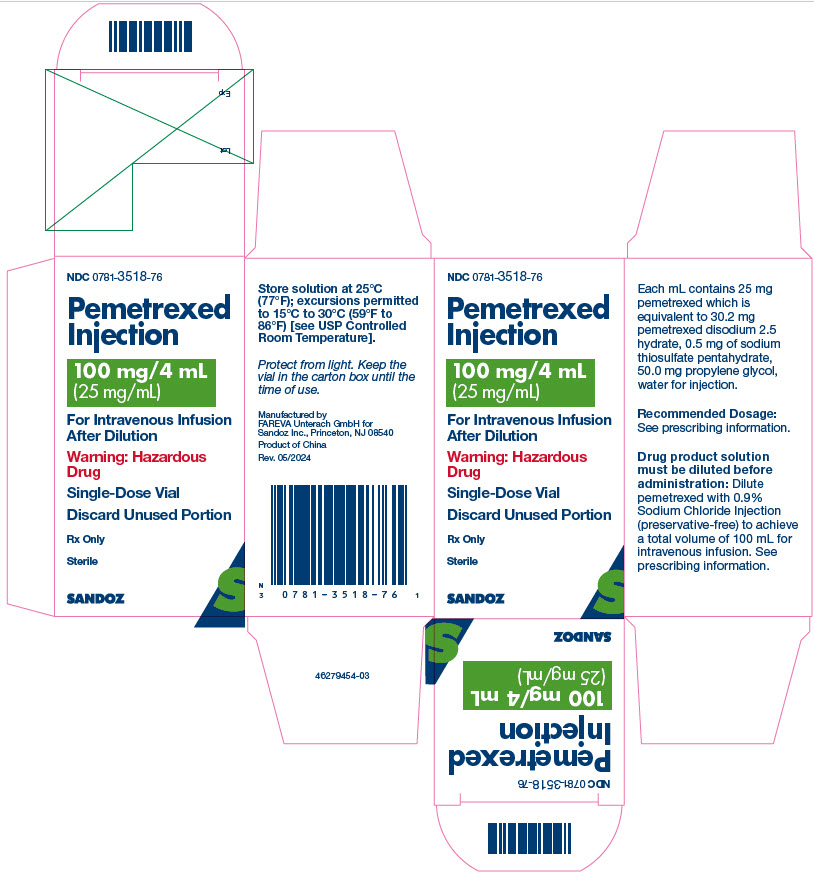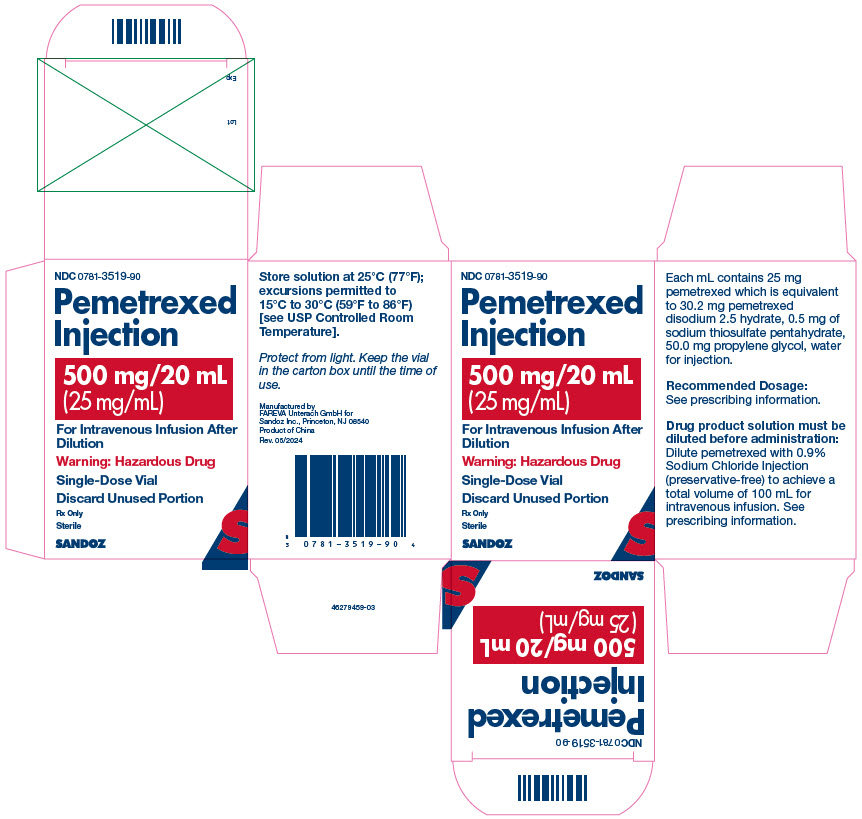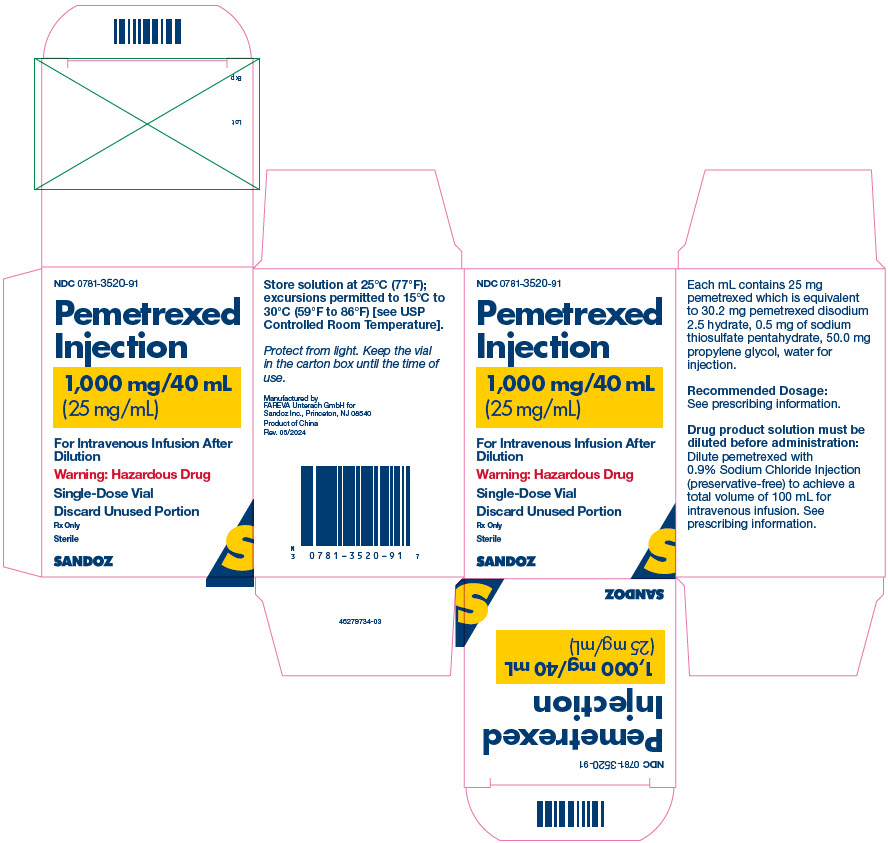 DRUG LABEL: Pemetrexed
NDC: 0781-3518 | Form: INJECTION, SOLUTION
Manufacturer: Sandoz Inc.
Category: prescription | Type: HUMAN PRESCRIPTION DRUG LABEL
Date: 20251216

ACTIVE INGREDIENTS: PEMETREXED DISODIUM 100 mg/4 mL
INACTIVE INGREDIENTS: SODIUM THIOSULFATE; HYDROCHLORIC ACID; SODIUM HYDROXIDE; WATER; PROPYLENE GLYCOL

HIGHLIGHTS OF PRESCRIBING INFORMATION

These highlights do not include all the information needed to use PEMETREXED INJECTION safely and effectively. See full prescribing information for PEMETREXED INJECTION.
PEMETREXED injection, for intravenous use
Initial U.S. Approval: 2004

1 INDICATIONS AND USAGE

Pemetrexed Injection is a folate analog metabolic inhibitor indicated:

- in combination with pembrolizumab and platinum chemotherapy, for the initial treatment of patients with metastatic non-squamous non-small cell lung cancer (NSCLC), with no EGFR or ALK genomic tumor aberrations. (1.1)
- in combination with cisplatin for the initial treatment of patients with locally advanced or metastatic, non-squamous NSCLC. (1.1)
- as a single agent for the maintenance treatment of patients with locally advanced or metastatic, non-squamous NSCLC whose disease has not progressed after four cycles of platinum-based first-line chemotherapy. (1.1)
- as a single agent for the treatment of patients with recurrent, metastatic non-squamous, NSCLC after prior chemotherapy. (1.1)

Limitations of Use: Pemetrexed Injection is not indicated for the treatment of patients with squamous cell, non-small cell lung cancer. (1.1)

- initial treatment, in combination with cisplatin, of patients with malignant pleural mesothelioma whose disease is unresectable or who are otherwise not candidates for curative surgery. (1.2)

2 DOSAGE AND ADMINISTRATION

- The recommended dosage of Pemetrexed Injection administered with pembrolizumab and platinum chemotherapy in patients with a creatinine clearance (calculated by Cockcroft-Gault equation) of 45 mL/min or greater is 500 mg/m^2 as an intravenous infusion over 10 minutes, administered after pembrolizumab and prior to platinum chemotherapy, on Day 1 of each 21-day cycle. (2.1)
- The recommended dosage of Pemetrexed Injection, administered as a single agent or with cisplatin, in patients with creatinine clearance of 45 mL/minute or greater is 500 mg/m^2 as an intravenous infusion over 10 minutes on Day 1 of each 21-day cycle. (2.1, 2.2)
- Initiate folic acid 400 mcg to 1000 mcg orally, once daily, beginning 7 days prior to the first dose of Pemetrexed Injection and continue until 21 days after the last dose of Pemetrexed Injection. (2.4)
- Administer vitamin B12, 1 mg intramuscularly, 1 week prior to the first dose of Pemetrexed Injection and every 3 cycles. (2.4)
- Administer dexamethasone 4 mg orally, twice daily the day before, the day of, and the day after Pemetrexed Injection administration. (2.4)

3 DOSAGE FORMS AND STRENGTHS

Injection: 100 mg/4 mL (25 mg/mL), 500 mg/20 mL (25 mg/mL), 1000 mg/40 mL (25 mg/mL) in single-dose vials. (3)

4 CONTRAINDICATIONS

History of severe hypersensitivity reaction to pemetrexed. (4)

5 WARNINGS AND PRECAUTIONS

- Myelosuppression: Can cause severe bone marrow suppression resulting in cytopenia and an increased risk of infection. Do not administer Pemetrexed Injection when the absolute neutrophil count is less than 1500 cells/mm^3 and platelets are less than 100,000 cells/mm^3. Initiate supplementation with oral folic acid and intramuscular vitamin B12 to reduce the severity of hematologic and gastrointestinal toxicity of Pemetrexed Injection. (2.4, 5.1)
- Renal Failure: Can cause severe, and sometimes fatal, renal failure. Do not administer when creatinine clearance is less than 45 mL/min. (2.3, 5.2)
- Bullous and Exfoliative Skin Toxicity: Permanently discontinue for severe and life-threatening bullous, blistering or exfoliating skin toxicity. (5.3)
- Interstitial Pneumonitis: Withhold for acute onset of new or progressive unexplained pulmonary symptoms. Permanently discontinue if pneumonitis is confirmed. (5.4)
- Radiation Recall: Can occur in patients who received radiation weeks to years previously; permanently discontinue for signs of radiation recall. (5.5)
- Embryo-Fetal Toxicity: Can cause fetal harm. Advise patients of the potential risk to a fetus and to use effective contraception. (5.7, 8.1, 8.3)

6 ADVERSE REACTIONS

- The most common adverse reactions (incidence ≥20%) of pemetrexed, when administered as a single agent are fatigue, nausea, and anorexia. (6.1)
- The most common adverse reactions (incidence ≥ 20%) of pemetrexed when administered with cisplatin are vomiting, neutropenia, anemia, stomatitis/pharyngitis, thrombocytopenia, and constipation. (6.1)
- The most common adverse reactions (incidence ≥ 20%) of pemetrexed when administered in combination with pembrolizumab and platinum chemotherapy are fatigue/asthenia, nausea, constipation, diarrhea, decreased appetite, rash, vomiting, cough, dyspnea, and pyrexia. (6.1)

To report SUSPECTED ADVERSE REACTIONS, contact Sandoz Inc. 1-800-525-8747 or FDA at 1-800-FDA-1088 or www.fda.gov/medwatch.

7 DRUG INTERACTIONS

OAT3 Inhibitors: Modify the ibuprofen dosage as recommended. Avoid other OAT3 inhibitors. (2.5, 5.6, 7)

8 USE IN SPECIFIC POPULATIONS

Lactation: Advise not to breastfeed. (8.2)

FULL PRESCRIBING INFORMATION

1 INDICATIONS AND USAGE

1.1 Non-Squamous Non-Small Cell Lung Cancer (NSCLC)

Pemetrexed Injection is indicated:

- in combination with pembrolizumab and platinum chemotherapy, for the initial treatment of patients with metastatic non-squamous non-small cell lung cancer (NSCLC), with no EGFR or ALK genomic tumor aberrations.
- in combination with cisplatin for the initial treatment of patients with locally advanced or metastatic, non-squamous NSCLC.
- as a single agent for the maintenance treatment of patients with locally advanced or metastatic, non-squamous NSCLC whose disease has not progressed after four cycles of platinum-based first-line chemotherapy.
- as a single agent for the treatment of patients with recurrent, metastatic non-squamous, NSCLC after prior chemotherapy.

Limitations of Use

Pemetrexed Injection is not indicated for the treatment of patients with squamous cell, non-small cell lung cancer [see Clinical Studies (14.1)].

1.2 Mesothelioma

Pemetrexed Injection is indicated, in combination with cisplatin, for the initial treatment of patients with malignant pleural mesothelioma whose disease is unresectable or who are otherwise not candidates for curative surgery.

2 DOSAGE AND ADMINISTRATION

2.1 Premedication and Concomitant Medications to Mitigate Toxicity

Vitamin Supplementation

- Initiate folic acid 400 mcg to 1000 mcg orally once daily, beginning 7 days before the first dose of Pemetrexed Injection and continuing until 21 days after the last dose of Pemetrexed Injection [see Warnings and Precautions (5.1)].
- Administer vitamin B12, 1 mg intramuscularly, 1 week prior to the first dose of Pemetrexed Injection and every 3 cycles thereafter. Subsequent vitamin B12 injections may be given the same day as treatment with Pemetrexed Injection [see Warnings and Precautions (5.1)]. Do not substitute oral vitamin B12 for intramuscular vitamin B12.

Corticosteroids

- Administer dexamethasone 4 mg orally twice daily for three consecutive days, beginning the day before each Pemetrexed Injection administration.

2.2 Recommended Dosage and Administration

Non-Squamous NSCLC

- The recommended dosage of Pemetrexed Injection when administered with pembrolizumab and platinum chemotherapy for the initial treatment of metastatic non-squamous NSCLC in patients with a creatinine clearance (calculated by Cockcroft-Gault equation) of 45 mL/min or greater is 500 mg/m^2 as an intravenous infusion over 10 minutes administered after pembrolizumab and prior to carboplatin or cisplatin on Day 1 of each 21-day cycle for 4 cycles. Following completion of platinum-based therapy, treatment with Pemetrexed Injection with or without pembrolizumab is administered until disease progression or unacceptable toxicity. Please refer to the full prescribing information for pembrolizumab and for carboplatin or cisplatin.
- The recommended dosage of Pemetrexed Injection when administered with cisplatin for initial treatment of locally advanced or metastatic non-squamous NSCLC in patients with a creatinine clearance (calculated by Cockcroft-Gault equation) of 45 mL/min or greater is 500 mg/m^2 as an intravenous infusion over 10 minutes administered prior to cisplatin on Day 1 of each 21-day cycle for up to six cycles in the absence of disease progression or unacceptable toxicity.
- The recommended dosage of Pemetrexed Injection for maintenance treatment of non-squamous NSCLC in patients with a creatinine clearance (calculated by Cockcroft-Gault equation) of 45 mL/min or greater is 500 mg/m^2 as an intravenous infusion over 10 minutes on Day 1 of each 21-day cycle until disease progression or unacceptable toxicity after four cycles of platinum based first-line chemotherapy.
- The recommended dosage of Pemetrexed Injection for treatment of recurrent non-squamous NSCLC in patients with a creatinine clearance (calculated by Cockcroft-Gault equation) of 45 mL/min or greater is 500 mg/m^2 as an intravenous infusion over 10 minutes on Day 1 of each 21-day cycle until disease progression or unacceptable toxicity.

Mesothelioma

- The recommended dosage of Pemetrexed Injection when administered with cisplatin in patients with a creatinine clearance (calculated by Cockcroft-Gault equation) of 45 mL/min or greater is 500 mg/m^2 as an intravenous infusion over 10 minutes on Day 1 of each 21-day cycle until disease progression or unacceptable toxicity.

2.3 Dosage Modifications for Adverse Reactions

Obtain complete blood count on Days 1, 8, and 15 of each cycle. Assess creatinine clearance prior to each cycle. Do not administer Pemetrexed Injection if the creatinine clearance is less than 45 mL/min.

Delay initiation of the next cycle of Pemetrexed Injection until:

- recovery of non-hematologic toxicity to Grade 0-2,
- absolute neutrophil count (ANC) is 1500 cells/mm3 or higher, and
- platelet count is 100,000 cells/mm3 or higher.

Upon recovery, modify the dosage of Pemetrexed Injection in the next cycle as specified in Table 1.

For dosing modifications for cisplatin, carboplatin, or pembrolizumab, refer to their prescribing information.

Table 1: Recommended Dosage Modifications for Adverse Reactions*

Toxicity in Most Recent Treatment Cycle | Pemetrexed Injection Dose Modification for Next Cycle
Myelosuppressive toxicity [see Warnings and Precautions (5.1)]
ANC less than 500/mm^3 and platelets greater than or equal to 50,000/mm^3 OR Platelet count less than 50,000/mm^3 without bleeding. | 75% of previous dose
Platelet count less than 50,000/mm^3 with bleeding | 50% of previous dose
Recurrent Grade 3 or 4 myelosuppression after 2 dose reductions | Discontinue
Non-hematologic toxicity
Any Grade 3 or 4 toxicities EXCEPT mucositis or neurologic toxicity OR Diarrhea requiring hospitalization | 75% of previous dose
Grade 3 or 4 mucositis | 50% of previous dose
Renal toxicity [see Warnings and Precautions (5.2)] | Withhold until creatinine clearance is 45 mL/min or greater
Grade 3 or 4 neurologic toxicity | Permanently discontinue
Recurrent Grade 3 or 4 non-hematologic toxicity after 2 dose reductions | Permanently discontinue
Severe and life-threatening Skin Toxicity [see Warnings and Precautions (5.3)] | Permanently discontinue
Interstitial Pneumonitis [see Warnings and Precautions (5.4)] | Permanently discontinue

*National Cancer Institute Common Toxicity Criteria for Adverse Events version 2 (NCI CTCAE v2).

2.4 Dosage Modifications for OAT3 Inhibitors

Avoid concomitant administration of ibuprofen for 2 days before, the day of, and 2 days following administration of Pemetrexed Injection [see Warnings and Precautions (5.6) and Drug Interactions (7)]. Avoid concomitant administration of other OAT3 inhibitors with Pemetrexed Injection. If concomitant administration cannot be avoided, monitor patients more frequently for myelosuppression, renal, and gastrointestinal toxicity.

2.5 Preparation for Administration

Pemetrexed Injection is a hazardous drug. Follow applicable special handling and disposal procedures.^1

- Calculate the dose of Pemetrexed Injection and determine the number of vials needed.
- Withdraw the calculated dose of Pemetrexed Injection from the vial(s) and discard vial with any unused portion.
- Further dilute Pemetrexed Injection with 0.9% Sodium Chloride Injection, USP (preservative–free) to achieve a total volume of 100 mL for intravenous infusion.
- Visually inspect for particulate matter and discoloration prior to administration, whenever solution and container permit. Discard if particulate matter or discoloration is observed.
- Administer Pemetrexed Injection as an intravenous infusion over 10 minutes.
- If not used immediately, store diluted product under refrigerated conditions [2°C to 8°C (36°F to 46°F)] for no more than 24 hours from the time of dilution. Discard after 24 hours.

3 DOSAGE FORMS AND STRENGTHS

Injection: Pemetrexed Injection is a clear, colorless to yellow or green-yellow solution available in sterile single-dose vials as follows:

- 100 mg/4 mL (25 mg/mL)
- 500 mg/20 mL (25 mg/mL)
- 1000 mg/40 mL (25 mg/mL)

4 CONTRAINDICATIONS

Pemetrexed Injection is contraindicated in patients with a history of severe hypersensitivity reaction to pemetrexed [see Adverse Reactions (6.1)].

5 WARNINGS AND PRECAUTIONS

5.1 Myelosuppression and Increased Risk of Myelosuppression without Vitamin Supplementation

Pemetrexed can cause severe myelosuppression resulting in a requirement for transfusions and which may lead to neutropenic infection. The risk of myelosuppression is increased in patients who do not receive vitamin supplementation. In Study JMCH, incidences of Grade 3 to 4 neutropenia (38% versus 23%), thrombocytopenia (9% versus 5%), febrile neutropenia (9% versus 0.6%), and neutropenic infection (6% versus 0) were higher in patients who received pemetrexed plus cisplatin without vitamin supplementation as compared to patients who were fully supplemented with folic acid and vitamin B12 prior to and throughout pemetrexed plus cisplatin treatment.

Initiate supplementation with oral folic acid and intramuscular vitamin B12 prior to the first dose of Pemetrexed Injection; continue vitamin supplementation during treatment and for 21 days after the last dose of Pemetrexed Injection to reduce the severity of hematologic and gastrointestinal toxicity of Pemetrexed Injection [see Dosage and Administration (2.4)].

Obtain a complete blood count at the beginning of each cycle. Do not administer Pemetrexed Injection until the ANC is at least 1500 cells/mm^3 and platelet count is at least 100,000 cells/mm^3. Permanently reduce Pemetrexed Injection in patients with an ANC of less than 500 cells/mm^3 or platelet count of less than 50,000 cells/mm^3 in previous cycles [see Dosage and Administration (2.6)].

In Studies JMDB and JMCH, among patients who received vitamin supplementation, incidence of Grade 3 to 4 neutropenia was 15% and 23%, the incidence of Grade 3 to 4 anemia was 6% and 4%, and incidence of Grade 3 to 4 thrombocytopenia was 4% and 5%, respectively. In Study JMCH, 18% of patients in the pemetrexed arm required red blood cell transfusions compared to 7% of patients in the cisplatin arm [see Adverse Reactions (6.1)]. In Studies JMEN, PARAMOUNT, and JMEI, where all patients received vitamin supplementation, incidence of Grade 3 to 4 neutropenia ranged from 3% to 5%, and incidence of Grade 3 to 4 anemia ranged from 3% to 5%.

5.2 Renal Failure

Pemetrexed can cause severe, and sometimes fatal, renal toxicity. The incidences of renal failure in clinical studies in which patients received pemetrexed with cisplatin were: 2.1% in Study JMDB and 2.2% in Study JMCH. The incidence of renal failure in clinical studies in which patients received pemetrexed as a single agent ranged from 0.4% to 0.6% (Studies JMEN, PARAMOUNT, and JMEI [see Adverse Reactions (6.1)]. Determine creatinine clearance before each dose and periodically monitor renal function during treatment with Pemetrexed Injection. Withhold Pemetrexed Injection in patients with a creatinine clearance of less than 45 mL/minute [see Dosage and Administration (2.3)].

5.3 Bullous and Exfoliative Skin Toxicity

Serious and sometimes fatal, bullous, blistering and exfoliative skin toxicity, including cases suggestive of Stevens-Johnson Syndrome/Toxic epidermal necrolysis can occur with pemetrexed. Permanently discontinue Pemetrexed Injection for severe and life-threatening bullous, blistering or exfoliating skin toxicity.

5.4 Interstitial Pneumonitis

Serious interstitial pneumonitis, including fatal cases, can occur with pemetrexed treatment. Withhold Pemetrexed Injection for acute onset of new or progressive unexplained pulmonary symptoms such as dyspnea, cough, or fever pending diagnostic evaluation. If pneumonitis is confirmed, permanently discontinue Pemetrexed Injection.

5.5 Radiation Recall

Radiation recall can occur with pemetrexed in patients who have received radiation weeks to years previously. Monitor patients for inflammation or blistering in areas of previous radiation treatment. Permanently discontinue Pemetrexed Injection for signs of radiation recall.

5.6 Increased Risk of Toxicity with Ibuprofen in Patients with Renal Impairment

Exposure to pemetrexed is increased in patients with mild to moderate renal impairment who take concomitant ibuprofen, increasing the risks of adverse reactions of pemetrexed. In patients with creatinine clearances between 45 mL/min and 79 mL/min, avoid administration of ibuprofen for 2 days before, the day of, and 2 days following administration of Pemetrexed Injection. If concomitant ibuprofen use cannot be avoided, monitor patients more frequently for Pemetrexed Injection adverse reactions, including myelosuppression, renal, and gastrointestinal toxicity [see Dosage and Administration (2.5), Drug Interactions (7), and Clinical Pharmacology (12.3)].

5.7 Embryo-Fetal Toxicity

Based on findings from animal studies and its mechanism of action, pemetrexed can cause fetal harm when administered to a pregnant woman. In animal reproduction studies, intravenous administration of pemetrexed to pregnant mice during the period of organogenesis was teratogenic, resulting in developmental delays and increased malformations at doses lower than the recommended human dose of 500 mg/m^2. Advise pregnant women of the potential risk to a fetus. Advise females of reproductive potential to use effective contraception during treatment with Pemetrexed Injection and for 6 months after the last dose. Advise males with female partners of reproductive potential to use effective contraception during treatment with Pemetrexed Injection and for 3 months after the last dose [see Use in Specific Populations (8.1, 8.3) and Clinical Pharmacology (12.1)].

6 ADVERSE REACTIONS

The following adverse reactions are discussed in greater detail in other sections of the labeling:

- Myelosuppression [see Warnings and Precautions (5.1)]
- Renal failure [see Warnings and Precautions (5.2)]
- Bullous and exfoliative skin toxicity [see Warning and Precautions (5.3)]
- Interstitial pneumonitis [see Warnings and Precautions (5.4)]
- Radiation recall [see Warnings and Precautions (5.5)]

6.1 Clinical Trials Experience

Because clinical trials are conducted under widely varying conditions, adverse reactions rates cannot be directly compared to rates in other clinical trials and may not reflect the rates observed in clinical practice.

In clinical trials, the most common adverse reactions (incidence ≥20%) of pemetrexed, when administered as a single agent, are fatigue, nausea, and anorexia. The most common adverse reactions (incidence ≥20%) of pemetrexed, when administered in combination with cisplatin are vomiting, neutropenia, anemia, stomatitis/pharyngitis, thrombocytopenia, and constipation. The most common adverse reactions (incidence ≥20%) of pemetrexed, when administered in combination with pembrolizumab and platinum chemotherapy, are fatigue/asthenia, nausea, constipation, diarrhea, decreased appetite, rash, vomiting, cough, dyspnea, and pyrexia.

Non-Squamous NSCLC

First-line Treatment of Metastatic Non-squamous NSCLC with Pembrolizumab and Platinum Chemotherapy

The safety of pemetrexed, in combination with pembrolizumab and investigator’s choice of platinum (either carboplatin or cisplatin), was investigated in Study KEYNOTE-189, a multicenter, double-blind, randomized (2:1), active-controlled trial in patients with previously untreated, metastatic non-squamous NSCLC with no EGFR or ALK genomic tumor aberrations. A total of 607 patients received pemetrexed, pembrolizumab, and platinum every 3 weeks for 4 cycles followed by pemetrexed and pembrolizumab (n=405), or placebo, pemetrexed, and platinum every 3 weeks for 4 cycles followed by placebo and pemetrexed (n=202). Patients with autoimmune disease that required systemic therapy within 2 years of treatment; a medical condition that required immunosuppression; or who had received more than 30 Gy of thoracic radiation within the prior 26 weeks were ineligible [see Clinical Studies (14.1)].

The median duration of exposure to pemetrexed was 7.2 months (range: 1 day to 1.7 years). Seventy-two percent of patients received carboplatin. The study population characteristics were: median age of 64 years (range: 34 to 84), 49% age 65 years or older, 59% male, 94% White and 3% Asian, and 18% with history of brain metastases at baseline.

Pemetrexed was discontinued for adverse reactions in 23% of patients in the pemetrexed, pembrolizumab, and platinum arm. The most common adverse reactions resulting in discontinuation of pemetrexed in this arm were acute kidney injury (3%) and pneumonitis (2%). Adverse reactions leading to interruption of pemetrexed occurred in 49% of patients in the pemetrexed, pembrolizumab, and platinum arm. The most common adverse reactions or laboratory abnormalities leading to interruption of pemetrexed in this arm (≥2%) were neutropenia (12%), anemia (7%), asthenia (4%), pneumonia (4%), thrombocytopenia (4%), increased blood creatinine (3%), diarrhea (3%), and fatigue (3%).

Table 2 summarizes the adverse reactions that occurred in ≥20% of patients treated with pemetrexed, pembrolizumab, and platinum.

Table 2: Adverse Reactions Occurring in ≥20% of Patients in KEYNOTE-189

 | Pemetrexed; Pembrolizumab; Platinum Chemotherapy; n=405 |  | Placebo; Pemetrexed; Platinum Chemotherapy; n=202
Adverse Reaction | All Grades*; (%) | Grade 3-4; (%) | All Grades; (%) | Grade 3-4; (%)
Gastrointestinal Disorders
Nausea | 56 | 3.5 | 52 | 3.5
Constipation | 35 | 1.0 | 32 | 0.5
Diarrhea | 31 | 5 | 21 | 3.0
Vomiting | 24 | 3.7 | 23 | 3.0
General Disorders and Administration Site Conditions
Fatigue† | 56 | 12 | 58 | 6
Pyrexia | 20 | 0.2 | 15 | 0
Metabolism and Nutrition Disorders
Decreased appetite | 28 | 1.5 | 30 | 0.5
Skin and Subcutaneous Tissue Disorders
Rash‡ | 25 | 2.0 | 17 | 2.5
Respiratory, Thoracic and Mediastinal Disorders
Cough | 21 | 0 | 28 | 0
Dyspnea | 21 | 3.7 | 26 | 5

*Graded per NCI CTCAE version 4.03.

†Includes asthenia and fatigue.

‡Includes genital rash, rash, rash generalized, rash macular, rash maculo-papular, rash papular, rash pruritic, and rash pustular.

Table 3 summarizes the laboratory abnormalities that worsened from baseline in at least 20% of patients treated with pemetrexed, pembrolizumab, and platinum.

Table 3: Laboratory Abnormalities Worsened from Baseline in ≥20% of Patients in KEYNOTE-189

 | Pemetrexed; Pembrolizumab; Platinum Chemotherapy |  | Placebo; Pemetrexed; Platinum Chemotherapy
Laboratory Test* | All Grades†; % | Grades 3-4; % | All Grades; % | Grades 3-4; %
Chemistry
Hyperglycemia | 63 | 9 | 60 | 7
Increased ALT | 47 | 3.8 | 42 | 2.6
Increased AST | 47 | 2.8 | 40 | 1.0
Hypoalbuminemia | 39 | 2.8 | 39 | 1.1
Increased creatinine | 37 | 4.2 | 25 | 1.0
Hyponatremia | 32 | 7 | 23 | 6
Hypophosphatemia | 30 | 10 | 28 | 14
Increased alkaline phosphatase | 26 | 1.8 | 29 | 2.1
Hypocalcemia | 24 | 2.8 | 17 | 0.5
Hyperkalemia | 24 | 2.8 | 19 | 3.1
Hypokalemia | 21 | 5 | 20 | 5
Hematology
Anemia | 85 | 17 | 81 | 18
Lymphopenia | 64 | 22 | 64 | 25
Neutropenia | 48 | 20 | 41 | 19
Thrombocytopenia | 30 | 12 | 29 | 8

*Each test incidence is based on the number of patients who had both baseline and at least one on-study laboratory measurement available: pemetrexed/pembrolizumab/platinum chemotherapy (range: 381 to 401 patients) and placebo/pemetrexed/platinum chemotherapy (range: 184 to 197 patients).

†Graded per NCI CTCAE version 4.03.

Initial Treatment in Combination with Cisplatin

The safety of pemetrexed was evaluated in Study JMDB, a randomized (1:1), open-label, multicenter trial conducted in chemotherapy-naive patients with locally advanced or metastatic NSCLC. Patients received either pemetrexed 500 mg/m^2 intravenously and cisplatin 75 mg/m^2 intravenously on Day 1 of each 21-day cycle (n=839) or gemcitabine 1250 mg/m^2 intravenously on Days 1 and 8 and cisplatin 75 mg/m^2 intravenously on Day 1 of each 21-day cycle (n=830). All patients were fully supplemented with folic acid and vitamin B12.

Study JMDB excluded patients with an Eastern Cooperative Oncology Group Performance Status (ECOG PS of 2 or greater), uncontrolled third-space fluid retention, inadequate bone marrow reserve and organ function, or a calculated creatinine clearance less than 45 mL/min. Patients unable to stop using aspirin or other non-steroidal anti-inflammatory drugs or unable to take folic acid, vitamin B12 or corticosteroids were also excluded from the study.

The data described below reflect exposure to pemetrexed plus cisplatin in 839 patients in Study JMDB. Median age was 61 years (range 26 to 83 years); 70% of patients were men; 78% were White,16% were Asian, 2.9% were Hispanic or Latino, 2.1% were Black or African American, and <1% were other ethnicities; 36% had an ECOG PS 0. Patients received a median of 5 cycles of pemetrexed.

Table 4 provides the frequency and severity of adverse reactions that occurred in ≥5% of 839 patients receiving pemetrexed in combination with cisplatin in Study JMDB. Study JMDB was not designed to demonstrate a statistically significant reduction in adverse reaction rates for pemetrexed, as compared to the control arm, for any specified adverse reaction listed in Table 4.

Table 4: Adverse Reactions Occurring in ≥5% of Fully Vitamin-Supplemented Patients Receiving Pemetrexed in Combination with Cisplatin Chemotherapy in Study JMDB

Adverse Reaction* | Pemetrexed /Cisplatin (N=839) |  | Gemcitabine/Cisplatin (N=830)
Adverse Reaction* | All Grades (%) | Grade 3-4 (%) | All Grades (%) | Grade 3-4 (%)
All adverse reactions | 90 | 37 | 91 | 53
Laboratory
Hematologic
Anemia | 33 | 6 | 46 | 10
Neutropenia | 29 | 15 | 38 | 27
Thrombocytopenia | 10 | 4 | 27 | 13
Renal
Elevated creatinine | 10 | 1 | 7 | 1
Clinical
Constitutional symptoms
Fatigue | 43 | 7 | 45 | 5
Gastrointestinal
Nausea | 56 | 7 | 53 | 4
Vomiting | 40 | 6 | 36 | 6
Anorexia | 27 | 2 | 24 | 1
Constipation | 21 | 1 | 20 | 0
Stomatitis/pharyngitis | 14 | 1 | 12 | 0
Diarrhea | 12 | 1 | 13 | 2
Dyspepsia/heartburn | 5 | 0 | 6 | 0
Neurology
Sensory neuropathy | 9 | 0 | 12 | 1
Taste disturbance | 8 | 0 | 9 | 0
Dermatology/Skin
Alopecia | 12 | 0 | 21 | 1
Rash/Desquamation | 7 | 0 | 8 | 1
*NCI CTCAE version 2.0.

The following additional adverse reactions of pemetrexed were observed.

Incidence 1% to <5%
Body as a Whole — febrile neutropenia, infection, pyrexia
General Disorders — dehydration
Metabolism and Nutrition — increased AST, increased ALT
Renal —renal failure
Eye Disorder — conjunctivitis
Incidence <1%
Cardiovascular — arrhythmia
General Disorders — chest pain
Metabolism and Nutrition — increased GGT
Neurology — motor neuropathy

Maintenance Treatment Following First-line Non-Pemetrexed Containing Platinum-Based Chemotherapy

In Study JMEN, the safety of pemetrexed was evaluated in a randomized (2:1), placebo-controlled, multicenter trial conducted in patients with non-progressive locally advanced or metastatic NSCLC following four cycles of a first-line, platinum-based chemotherapy regimen. Patients received either pemetrexed 500 mg/m^2 or matching placebo intravenously every 21 days until disease progression or unacceptable toxicity. Patients in both study arms were fully supplemented with folic acid and vitamin B12.

Study JMEN excluded patients with an ECOG PS of 2 or greater, uncontrolled third-space fluid retention, inadequate bone marrow reserve and organ function, or a calculated creatinine clearance less than 45 mL/min. Patients unable to stop using aspirin or other non-steroidal anti-inflammatory drugs or unable to take folic acid, vitamin B12 or corticosteroids were also excluded from the study.

The data described below reflect exposure to pemetrexed in 438 patients in Study JMEN. Median age was 61 years (range 26-83 years), 73% of patients were men; 65% were White, 31% were Asian, 2.9% were Hispanic or Latino, and <2% were other ethnicities; 39% had an ECOG PS 0. Patients received a median of 5 cycles of pemetrexed and a relative dose intensity of pemetrexed of 96%. Approximately half the patients (48%) completed at least six, 21-day cycles and 23% completed ten or more 21-day cycles of pemetrexed.

Table 5 provides the frequency and severity of adverse reactions reported in ≥5% of the 438 pemetrexed-treated patients in Study JMEN.

Table 5: Adverse Reactions Occurring in ≥5% of Patients Receiving Pemetrexed in Study JMEN

Adverse Reaction* | Pemetrexed (N=438) |  | Placebo (N=218)
Adverse Reaction* | All Grades (%) | Grade 3-4 (%) | All Grades (%) | Grade 3-4 (%)
All adverse reactions | 66 | 16 | 37 | 4
Laboratory
Hematologic
Anemia | 15 | 3 | 6 | 1
Neutropenia | 6 | 3 | 0 | 0
Hepatic
Increased ALT | 10 | 0 | 4 | 0
Increased AST | 8 | 0 | 4 | 0
Clinical
Constitutional symptoms
Fatigue | 25 | 5 | 11 | 1
Gastrointestinal
Nausea | 19 | 1 | 6 | 1
Anorexia | 19 | 2 | 5 | 0
Vomiting | 9 | 0 | 1 | 0
Mucositis/stomatitis | 7 | 1 | 2 | 0
Diarrhea | 5 | 1 | 3 | 0
Infection | 5 | 2 | 2 | 0
Neurology
Sensory neuropathy | 9 | 1 | 4 | 0
Dermatology/Skin
Rash/desquamation | 10 | 0 | 3 | 0
*NCI CTCAE version 3.0.

The requirement for transfusions (9.5% versus 3.2%), primarily red blood cell transfusions, and for erythropoiesis stimulating agents (5.9% versus 1.8%) were higher in the pemetrexed arm compared to the placebo arm.

The following additional adverse reactions were observed in patients who received pemetrexed.

Incidence 1% to<5%
Dermatology/Skin — alopecia, pruritus/itching
Gastrointestinal — constipation
General Disorders — edema, fever
Hematologic — thrombocytopenia
Eye Disorder — ocular surface disease (including conjunctivitis), increased lacrimation
Incidence <1%
Cardiovascular — supraventricular arrhythmia
Dermatology/Skin — erythema multiforme
General Disorders — febrile neutropenia, allergic reaction/hypersensitivity
Neurology — motor neuropathy
Renal — renal failure

Maintenance Treatment Following First-line Pemetrexed Plus Platinum Chemotherapy

The safety of pemetrexed was evaluated in PARAMOUNT, a randomized (2:1), placebo-controlled study conducted in patients with non-squamous NSCLC with non-progressive (stable or responding disease) locally advanced or metastatic NSCLC following four cycles of pemetrexed in combination with cisplatin as first-line therapy for NSCLC. Patients were randomized to receive pemetrexed 500 mg/m^2 or matching placebo intravenously on Day 1 of each 21-day cycle until disease progression or unacceptable toxicity. Patients in both study arms received folic acid and vitamin B12 supplementation.

PARAMOUNT excluded patients with an ECOG PS of 2 or greater, uncontrolled third-space fluid retention, inadequate bone marrow reserve and organ function, or a calculated creatinine clearance less than 45 mL/min. Patients unable to stop using aspirin or other non-steroidal anti-inflammatory drugs or unable to take folic acid, vitamin B12 or corticosteroids were also excluded from the study.

The data described below reflect exposure to pemetrexed in 333 patients in PARAMOUNT. Median age was 61 years (range 32 to 83 years); 58% of patients were men; 94% were White, 4.8% were Asian, and <1% were Black or African American; 36% had an ECOG PS 0. The median number of maintenance cycles was 4 for pemetrexed and placebo arms. Dose reductions for adverse reactions occurred in 3.3% of patients in the pemetrexed arm and 0.6% in the placebo arm. Dose delays for adverse reactions occurred in 22% of patients in the pemetrexed arm and 16% in the placebo arm.

Table 6 provides the frequency and severity of adverse reactions reported in ≥5% of the 333 pemetrexed-treated patients in PARAMOUNT.

Table 6: Adverse Reactions Occurring in ≥5% of Patients Receiving Pemetrexed in PARAMOUNT
Adverse Reaction* | Pemetrexed (N=333) |  | Placebo (N=167)
Adverse Reaction* | All Grades (%) | Grade 3-4 (%) | All Grades (%) | Grades 3-4 (%)
All adverse reactions | 53 | 17 | 34 | 4.8
Laboratory
Hematologic
Anemia | 15 | 4.8 | 4.8 | 0.6
Neutropenia | 9 | 3.9 | 0.6 | 0
Clinical
Constitutional symptoms
Fatigue | 18 | 4.5 | 11 | 0.6
Gastrointestinal
Nausea | 12 | 0.3 | 2.4 | 0
Vomiting | 6 | 0 | 1.8 | 0
Mucositis/stomatitis | 5 | 0.3 | 2.4 | 0
General disorders
Edema | 5 | 0 | 3.6 | 0
*NCI CTCAE version 3.0.

The requirement for red blood cell (13% versus 4.8%) and platelet (1.5% versus 0.6%) transfusions, erythropoiesis stimulating agents (12% versus 7%), and granulocyte colony stimulating factors (6% versus 0%) were higher in the pemetrexed arm compared to the placebo arm.

The following additional Grade 3 or 4 adverse reactions were observed more frequently in the pemetrexed arm.

Incidence 1% to <5%
Blood/Bone Marrow — thrombocytopenia
General Disorders — febrile neutropenia
Incidence <1%
Cardiovascular — ventricular tachycardia, syncope
General Disorders — pain
Gastrointestinal — gastrointestinal obstruction
Neurologic — depression
Renal — renal failure
Vascular — pulmonary embolism

Treatment of Recurrent Disease After Prior Chemotherapy

The safety of pemetrexed was evaluated in Study JMEI, a randomized (1:1), open-label, active-controlled trial conducted in patients who had progressed following platinum-based chemotherapy. Patients received pemetrexed 500 mg/m^2 intravenously or docetaxel 75 mg/m^2 intravenously on Day 1 of each 21-day cycle. All patients on the pemetrexed arm received folic acid and vitamin B12 supplementation.

Study JMEI excluded patients with an ECOG PS of 3 or greater, uncontrolled third-space fluid retention, inadequate bone marrow reserve and organ function, or a calculated creatinine clearance less than 45 mL/min. Patients unable to discontinue aspirin or other non-steroidal anti-inflammatory drugs or unable to take folic acid, vitamin B12 or corticosteroids were also excluded from the study.

The data described below reflect exposure to pemetrexed in 265 patients in Study JMEI. Median age was 58 years (range 22 to 87 years); 73% of patients were men; 70% were White, 24% were Asian, 2.6% were Black or African American, 1.8% were Hispanic or Latino, and <2% were other ethnicities; 19% had an ECOG PS 0.

Table 7 provides the frequency and severity of adverse reactions reported in ≥5% of the 265 pemetrexed-treated patients in Study JMEI. Study JMEI is not designed to demonstrate a statistically significant reduction in adverse reaction rates for pemetrexed, as compared to the control arm, for any specified adverse reaction listed in the Table 7 below.

Table 7: Adverse Reactions Occurring in ≥5% of Fully Supplemented Patients Receiving Pemetrexed in Study JMEI
Adverse Reaction* | Pemetrexed (N=265) |  | Docetaxel (N=276)
Adverse Reaction* | All Grades (%) | Grades 3-4 (%) | All Grade (%) | Grades 3-4 (%)
Laboratory
Hematologic
Anemia | 19 | 4 | 22 | 4
Neutropenia | 11 | 5 | 45 | 40
Thrombocytopenia | 8 | 2 | 1 | 0
Hepatic
Increased ALT | 8 | 2 | 1 | 0
Increased AST | 7 | 1 | 1 | 0
Clinical
Gastrointestinal
Nausea | 31 | 3 | 17 | 2
Anorexia | 22 | 2 | 24 | 3
Vomiting | 16 | 2 | 12 | 1
Stomatitis/pharyngitis | 15 | 1 | 17 | 1
Diarrhea | 13 | 0 | 24 | 3
Constipation | 6 | 0 | 4 | 0
Constitutional symptoms
Fatigue | 34 | 5 | 36 | 5
Fever | 8 | 0 | 8 | 0
Dermatology/Skin
Rash/desquamation | 14 | 0 | 6 | 0
Pruritus | 7 | 0 | 2 | 0
Alopecia | 6 | 1 | 38 | 2
*NCI CTCAE version 2.0.

The following additional adverse reactions were observed in patients assigned to receive pemetrexed.

Incidence 1% to <5%
Body as a Whole — abdominal pain, allergic reaction/hypersensitivity, febrile neutropenia, infection
Dermatology/Skin — erythema multiforme
Neurology — motor neuropathy, sensory neuropathy
Incidence <1%
Cardiovascular — supraventricular arrhythmias
Renal — renal failure

Mesothelioma

The safety of pemetrexed was evaluated in Study JMCH, a randomized (1:1), single-blind study conducted in patients with MPM who had received no prior chemotherapy for MPM. Patients received pemetrexed 500 mg/m^2 intravenously in combination with cisplatin 75 mg/m^2 intravenously on Day 1 of each 21-day cycle or cisplatin 75 mg/m^2 intravenously on Day 1 of each 21-day cycle administered until disease progression or unacceptable toxicity. Safety was assessed in 226 patients who received at least one dose of pemetrexed in combination with cisplatin and 222 patients who received at least one dose of cisplatin alone. Among 226 patients who received pemetrexed in combination with cisplatin, 74% (n=168) received full supplementation with folic acid and vitamin B12 during study therapy, 14% (n=32) were never supplemented, and 12% (n=26) were partially supplemented.

Study JMCH excluded patients with Karnofsky Performance Scale (KPS) of less than 70, inadequate bone marrow reserve and organ function, or a calculated creatinine clearance less than 45 mL/min. Patients unable to stop using aspirin or other non-steroidal anti-inflammatory drugs were also excluded from the study.

The data described below reflect exposure to pemetrexed in 168 patients that were fully supplemented with folic acid and vitamin B12. Median age was 60 years (range 19 to 85 years); 82% were men; 92% were White, 5% were Hispanic or Latino, 3.0% were Asian, and <1% were other ethnicities; 54% had KPS of 90-100. The median number of treatment cycles administered was 6 in the pemetrexed/cisplatin fully supplemented group and 2 in the pemetrexed /cisplatin never supplemented group. Patients receiving pemetrexed in the fully supplemented group had a relative dose intensity of 93% of the protocol-specified pemetrexed dose intensity. The most common adverse reaction resulting in dose delay was neutropenia.

Table 8 provides the frequency and severity of adverse reactions ≥5% in the subgroup of pemetrexed-treated patients who were fully vitamin supplemented in Study JMCH. Study JMCH was not designed to demonstrate a statistically significant reduction in adverse reaction rates for pemetrexed, as compared to the control arm, for any specified adverse reaction listed in the table below.

Table 8: Adverse Reactions Occurring in ≥5% of Fully Supplemented Subgroup of Patients Receiving Pemetrexed/Cisplatin in Study JMCH*
Adverse Reaction† | Pemetrexed/cisplatin (N=168) |  | Cisplatin (N=163)
Adverse Reaction† | All Grades (%) | Grade 3-4 (%) | All Grades (%) | Grade 3-4 (%)
Laboratory
Hematologic
Neutropenia | 56 | 23 | 13 | 3
Anemia | 26 | 4 | 10 | 0
Thrombocytopenia | 23 | 5 | 9 | 0
Renal
Elevated creatinine | 11 | 1 | 10 | 1
Decreased creatinine clearance | 16 | 1 | 18 | 2
Clinical
Eye Disorder
Conjunctivitis | 5 | 0 | 1 | 0
Gastrointestinal
Nausea | 82 | 12 | 77 | 6
Vomiting | 57 | 11 | 50 | 4
Stomatitis/pharyngitis | 23 | 3 | 6 | 0
Anorexia | 20 | 1 | 14 | 1
Diarrhea | 17 | 4 | 8 | 0
Constipation | 12 | 1 | 7 | 1
Dyspepsia | 5 | 1 | 1 | 0
Constitutional Symptoms
Fatigue | 48 | 10 | 42 | 9
Metabolism and Nutrition
Dehydration | 7 | 4 | 1 | 1
Neurology
Sensory neuropathy | 10 | 0 | 10 | 1
Taste disturbance | 8 | 0 | 6 | 0
Dermatology/Skin
Rash | 16 | 1 | 5 | 0
Alopecia | 11 | 0 | 6 | 0
*In Study JMCH, 226 patients received at least one dose of pemetrexed in combination with cisplatin and 222 patients received at least one dose of cisplatin. Table 8 provides the ADRs for subgroup of patients treated with pemetrexed in combination with cisplatin (168 patients) or cisplatin alone (163 patients) who received full supplementation with folic acid and vitamin B12 during study therapy.
†NCI CTCAE version 2.0.

The following additional adverse reactions were observed in patients receiving pemetrexed plus cisplatin:

Incidence 1% to <5%
Body as a Whole — febrile neutropenia, infection, pyrexia
Dermatology/Skin — urticaria
General Disorders — chest pain
Metabolism and Nutrition — increased AST, increased ALT, increased GGT
Renal — renal failure
Incidence <1%
Cardiovascular — arrhythmia
Neurology — motor neuropathy

Exploratory Subgroup Analyses based on Vitamin Supplementation

Table 9 provides the results of exploratory analyses of the frequency and severity of NCI CTCAE Grade 3 or 4 adverse reactions reported in more pemetrexed-treated patients who did not receive vitamin supplementation (never supplemented) as compared with those who received vitamin supplementation with daily folic acid and vitamin B12 from the time of enrollment in Study JMCH (fully-supplemented).

Table 9: Exploratory Subgroup Analysis of Selected Grade 3/4 Adverse Reactions Occurring in Patients Receiving Pemetrexed in Combination with Cisplatin with or without Full Vitamin Supplementation in Study JMCH*

Grade 3-4 Adverse Reactions | Fully Supplemented Patients N=168 (%) | Never Supplemented Patients N=32 (%)
Neutropenia | 23 | 38
Thrombocytopenia | 5 | 9
Vomiting | 11 | 31
Febrile neutropenia | 1 | 9
Infection with Grade 3/4 neutropenia | 0 | 6
Diarrhea | 4 | 9
*NCI CTCAE version 2.0.

The following adverse reactions occurred more frequently in patients who were fully vitamin supplemented than in patients who were never supplemented:

- hypertension (11% versus 3%),
- chest pain (8% versus 6%),
- thrombosis/embolism (6% versus 3%).

Additional Experience Across Clinical Trials

Sepsis, with or without neutropenia, including fatal cases: 1%

Severe esophagitis, resulting in hospitalization: <1%

6.2 Postmarketing Experience

The following adverse reactions have been identified during post-approval use of pemetrexed. Because these reactions are reported voluntarily from a population of uncertain size, it is not always possible to reliably estimate their frequency or establish a causal relationship to drug exposure.

Blood and Lymphatic System — immune-mediated hemolytic anemia
Gastrointestinal — colitis, pancreatitis
General Disorders and Administration Site Conditions — edema
Injury, poisoning, and procedural complications — radiation recall
Respiratory — interstitial pneumonitis
Skin — Serious and fatal bullous skin conditions, Stevens-Johnson syndrome, and toxic epidermal necrolysis

7 DRUG INTERACTIONS

7.1 Effects of Other Drugs on Pemetrexed Injection

OAT3 Inhibitors

Avoid concomitant administration of ibuprofen for 2 days before, the day of, and 2 days following administration of Pemetrexed Injection [see Dosage and Administration (2.5)]. Avoid concomitant administration of other OAT3 inhibitors before and after administration of Pemetrexed Injection, when possible. If concomitant administration cannot be avoided, monitor patients more frequently for myelosuppression, renal, and gastrointestinal toxicity.

Pemetrexed is an OAT3 substrate [see Clinical Pharmacology (12.3)]. Concomitant use with an OAT3 inhibitor increases pemetrexed systemic exposure (AUC) [see Clinical Pharmacology (12.3)], which may increase the risk of Pemetrexed Injection adverse reactions.

8 USE IN SPECIFIC POPULATIONS

8.1 Pregnancy

Risk Summary

Based on findings from animal studies and its mechanism of action, pemetrexed can cause fetal harm when administered to a pregnant woman [see Clinical Pharmacology (12.1)]. There are no available data on Pemetrexed Injection use in pregnant women. In animal reproduction studies, intravenous administration of pemetrexed to pregnant mice during the period of organogenesis was teratogenic, resulting in developmental delays and malformations at doses lower than the recommended human dose of 500 mg/m^2 [see Data]. Advise pregnant women of the potential risk to a fetus [see Use in Special Populations (8.3)].

In the U.S. general population, the estimated background risk of major birth defects and miscarriage in clinically recognized pregnancies is 2 to 4% and 15 to 20%, respectively.

Data

Animal Data

Pemetrexed was teratogenic in mice. Daily dosing of pemetrexed by intravenous injection to pregnant mice during the period of organogenesis increased the incidence of fetal malformations (cleft palate; protruding tongue; enlarged or misshaped kidney; and fused lumbar vertebra) at doses (based on BSA) 0.03 times the human dose of 500 mg/m^2. At doses, based on BSA, greater than or equal to 0.0012 times the 500 mg/m^2 human dose, pemetrexed administration resulted in dose-dependent increases in developmental delays (incomplete ossification of talus and skull bone; and decreased fetal weight).

8.2 Lactation

Risk Summary

There is no information regarding the presence of pemetrexed or its metabolites in human milk, the effects on the breastfed infant, or the effects on milk production. Because of the potential for serious adverse reactions in breastfed infants from Pemetrexed Injection, advise women not to breastfeed during treatment with Pemetrexed Injection and for one week after the last dose.

8.3 Females and Males of Reproductive Potential

Based on animal data pemetrexed can cause malformations and developmental delays when administered to a pregnant woman [see Use in Specific Populations (8.1)].

Pregnancy Testing

Verify pregnancy status of females of reproductive potential prior to initiating Pemetrexed Injection [see Use in Specific Populations (8.1)].

Contraception

Females

Because of the potential for genotoxicity, advise females of reproductive potential to use effective contraception during treatment with Pemetrexed Injection and for 6 months after the last dose.

Males

Because of the potential for genotoxicity, advise males with female partners of reproductive potential to use effective contraception during treatment with Pemetrexed Injection and for 3 months after the last dose [see Nonclinical Toxicology (13.1)].

Infertility

Males

Pemetrexed may impair fertility in males of reproductive potential. It is not known whether these effects on fertility are reversible [see Nonclinical Toxicology (13.1)].

8.4 Pediatric Use

The safety and effectiveness of pemetrexed in pediatric patients have not been established.

The safety and pharmacokinetics of pemetrexed were evaluated in two clinical studies conducted in pediatric patients with recurrent solid tumors (NCT00070473, N=32 and NCT00520936, N=72). Patients in both studies received concomitant vitamin B12 and folic acid supplementation and dexamethasone.

No tumor responses were observed. No new safety signals were observed.

Single-dose pharmacokinetics of pemetrexed were evaluated in 22 patients aged 4 to 18 years enrolled in NCT00070473 were within range of values in adults.

8.5 Geriatric Use

Of the 3,946 patients enrolled in clinical studies of pemetrexed, 34% were 65 and over and 4% were 75 and over. No overall differences in effectiveness were observed between these patients and younger patients. The incidences of Grade 3 to 4 anemia, fatigue, thrombocytopenia, hypertension, and neutropenia were higher in patients 65 years of age and older as compared to younger patients: in at least one of five randomized clinical trials [see Adverse Reactions (6.1) and Clinical Studies (14.1, 14.2)].

10 OVERDOSAGE

No drugs are approved for the treatment of pemetrexed overdose. Based on animal studies, administration of leucovorin may mitigate the toxicities of pemetrexed overdosage. It is not known whether pemetrexed is dialyzable.

11 DESCRIPTION

Pemetrexed Injection is a folate analog metabolic inhibitor. The drug substance, pemetrexed disodium, has the chemical name N-[[4-[2-(2-Amino-4-oxo-4,7-dihydro-1H-pyrrolo[2,3-d]pyrimidin-5-yl)ethyl]phenyl] carbonyl] -L-glutamic acid disodium, 2.5H2O with a molecular formula of C20H19N5Na2O6 2.5 H2O and a molecular weight of 516.41 The structural formula is as follows:

Pemetrexed Injection is supplied as a sterile clear colorless to yellow or green-yellow solution for intravenous infusion available in single-dose vials.

Each mL contains 25 mg pemetrexed (30.2 mg pemetrexed disodium 2.5 hydrate), 0.5 mg sodium thiosulfate pentahydrate, 50 mg propylene glycol, water for injection. Hydrochloric acid and/or sodium hydroxide may have been added to adjust pH.

Pemetrexed Injection requires dilution prior to intravenous infusion. Pemetrexed Injection should be diluted in 0.9% sodium chloride injection (preservative-free) to achieve a total volume of 100 mL for intravenous infusion.

12 CLINICAL PHARMACOLOGY

12.1 Mechanism of Action

Pemetrexed is a folate analog metabolic inhibitor that disrupts folate-dependent metabolic processes essential for cell replication. In vitro studies show that pemetrexed inhibits thymidylate synthase (TS), dihydrofolate reductase, and glycinamide ribonucleotide formyltransferase (GARFT), which are folate-dependent enzymes involved in the de novo biosynthesis of thymidine and purine nucleotides. Pemetrexed is taken into cells by membrane carriers such as the reduced folate carrier and membrane folate binding protein transport systems. Once in the cell, pemetrexed is converted to polyglutamate forms by the enzyme folylpolyglutamate synthetase. The polyglutamate forms are retained in cells and are inhibitors of TS and GARFT.

12.2 Pharmacodynamics

The depth of the absolute neutrophil counts (ANC) nadir correlates with the systemic exposure to pemetrexed and supplementation with folic acid and vitamin B12. There is no cumulative effect of pemetrexed exposure on ANC nadir over multiple treatment cycles.

There is insufficient information to characterize the effect of Pemetrexed Injection on the QTc interval.

12.3 Pharmacokinetics

The pharmacokinetics of pemetrexed administered as a single agent in doses ranging from 0.2 to 838 mg/m^2 (0.0004 to 1.7 times the recommended dose) infused over a 10-minute period have been evaluated in patients with a variety of solid tumors. Pemetrexed total systemic exposure (AUC) and maximum plasma concentration (Cmax) increased in a dose proportional manner. Pemetrexed does not accumulate over multiple treatment cycles.

Distribution

Pemetrexed steady-state volume of distribution is 16 L. Pemetrexed plasma protein binding is 81% in vitro.

Elimination

Pemetrexed elimination half-life is 3.5 hours in patients with normal renal function [creatinine clearance (CLcr) of 90 mL/min] with a total systemic clearance of 92 mL/min. As renal function decreases, the clearance of pemetrexed decreases and AUC of pemetrexed increases.

Excretion

Pemetrexed is primarily eliminated in the urine, with 70% to 90% of the dose recovered unchanged within the first 24 hours following administration.

Specific Populations

No clinically significant differences in the pharmacokinetics of pemetrexed were observed based on age (26 to 80 years), sex and race (Whites and Blacks or African Americans).

Patients with Hepatic Impairment

No effect of elevated AST, ALT, or total bilirubin on the PK of pemetrexed was observed in clinical studies.

Patients with Renal Impairment

Plasma clearance of pemetrexed decreases as renal function decreases, with a resultant increase in systemic exposure. Patients with creatinine clearances of 45, 50, and 80 mL/min had 1.6, 1.5 and 1.1-fold increase, respectively in systemic exposure (AUC).

Third-Space Fluid

The pemetrexed plasma concentrations in patients with various solid tumors with stable, mild to moderate third-space fluid were comparable to those observed in patients without third space fluid collections. The effect of severe third space fluid on pharmacokinetics is not known.

Drug Interaction Studies

Clinical Studies

OAT3 Inhibitors: Pemetrexed systemic exposure (AUC) increased by approximately 1.2-fold in patients with CLcr >80 mL/min following concomitant administration of ibuprofen (OAT3 inhibitor) 400 mg four times a day.

Other Drugs: No clinically significant differences in pemetrexed pharmacokinetics were observed when used concomitantly with aspirin 325 mg every 6 hours, folic acid, vitamin B12 or cisplatin.

No clinically significant differences in the pharmacokinetics of the following drugs were observed when used concomitantly with pemetrexed: cisplatin.

In Vitro Studies

CYP450 Enzymes: Pemetrexed does not inhibit CYP3A, CYP2D6, CYP2C9, and CYP1A2.

Transporter Systems: Pemetrexed is a substrate of OAT4 and OAT3.

13 NONCLINICAL TOXICOLOGY

13.1 Carcinogenesis, Mutagenesis, Impairment of Fertility

No carcinogenicity studies have been conducted with pemetrexed. Pemetrexed was clastogenic in an in vivo micronucleus assay in mouse bone marrow but was not mutagenic in multiple in vitro tests (Ames assay, Chinese Hamster Ovary cell assay).

Pemetrexed administered intraperitoneally at doses of ≥0.1 mg/kg/day to male mice (approximately 0.0006 times the recommended human dose based on BSA) resulted in reduced fertility, hypospermia, and testicular atrophy.

14 CLINICAL STUDIES

14.1 Non-Squamous NSCLC

Initial Treatment in Combination with Pembrolizumab and Platinum

The efficacy of pemetrexed in combination with pembrolizumab and platinum chemotherapy was investigated in Study KEYNOTE-189 (NCT02578680), a randomized, multicenter, double-blind, active-controlled trial conducted in patients with metastatic non-squamous NSCLC, regardless of PD-L1 tumor expression status, who had not previously received systemic therapy for metastatic disease and in whom there were no EGFR or ALK genomic tumor aberrations. Patients with autoimmune disease that required systemic therapy within 2 years of treatment; a medical condition that required immunosuppression; or who had received more than 30 Gy of thoracic radiation within the prior 26 weeks were ineligible. Randomization was stratified by smoking status (never versus former/current), choice of platinum (cisplatin versus carboplatin), and tumor PD-L1 status (TPS <1% [negative] versus TPS ≥1%). Patients were randomized (2:1) to one of the following treatment arms:

- Pemetrexed 500 mg/m^2, pembrolizumab 200 mg, and investigator’s choice of cisplatin 75 mg/m^2 or carboplatin AUC 5 mg/mL/min intravenously on Day 1 of each 21-day cycle for 4 cycles followed by pemetrexed 500 mg/m^2 and pembrolizumab 200 mg intravenously every 3 weeks. Pemetrexed was administered after pembrolizumab and prior to platinum chemotherapy on Day 1.
- Placebo, pemetrexed 500 mg/m^2, and investigator’s choice of cisplatin 75 mg/m^2 or carboplatin AUC 5 mg/mL/min intravenously on Day 1 of each 21-day cycle for 4 cycles followed by placebo and pemetrexed 500 mg/m^2 intravenously every 3 weeks.

Treatment with pemetrexed continued until RECIST v1.1 (modified to follow a maximum of 10 target lesions and a maximum of 5 target lesions per organ)-defined progression of disease as determined by the investigator or unacceptable toxicity. Patients randomized to placebo, pemetrexed, and platinum chemotherapy were offered pembrolizumab as a single agent at the time of disease progression.

Assessment of tumor status was performed at Week 6, Week 12, and then every 9 weeks thereafter. The main efficacy outcome measures were OS and PFS as assessed by BICR RECIST v1.1, modified to follow a maximum of 10 target lesions and a maximum of five target lesions per organ. Additional efficacy outcome measures were ORR and duration of response, as assessed by the BICR according to RECIST v1.1, modified to follow a maximum of 10 target lesions and a maximum of 5 target lesions per organ.

A total of 616 patients were randomized: 410 patients to the pemetrexed, pembrolizumab, and platinum chemotherapy arm and 206 to the placebo, pemetrexed, and platinum chemotherapy arm. The study population characteristics were: median age of 64 years (range: 34 to 84); 49% age 65 or older; 59% male; 94% White and 3% Asian; 56% ECOG performance status of 1; and 18% with history of brain metastases. Thirty-one percent had tumor PD-L1 expression TPS <1%. Seventy-two percent received carboplatin and 12% were never smokers. A total of 85 patients in the placebo, pemetrexed, and chemotherapy arm received an anti-PD-1/PD-L1 monoclonal antibody at the time of disease progression.

The trial demonstrated a statistically significant improvement in OS and PFS for patients randomized to pemetrexed in combination with pembrolizumab and platinum chemotherapy compared with placebo, pemetrexed, and platinum chemotherapy (see Table 10 and Figure 1).

Table 10: Efficacy Results of KEYNOTE-189

Endpoint | Pemetrexed; Pembrolizumab; Platinum Chemotherapy; n=410 | Placebo; Pemetrexed; Platinum Chemotherapy; n=206
OS
Number (%) of patients with event | 127 (31%) | 108 (52%)
Median in months (95% CI) | NR; (NR, NR) | 11.3; (8.7, 15.1)
Hazard ratio* (95% CI) | 0.49 (0.38, 0.64)
p-value† | <0.0001
PFS
Number of patients with event (%) | 245 (60%) | 166 (81%)
Median in months (95% CI) | 8.8 (7.6, 9.2) | 4.9 (4.7, 5.5)
Hazard ratio* (95% CI) | 0.52 (0.43, 0.64)
p-value† | <0.0001
ORR
Overall response rate‡ (95% CI) | 48% (43, 53) | 19% (14, 25)
Complete response | 0.5% | 0.5%
Partial response | 47% | 18%
p-value§ | <0.0001
Duration of Response
Median in months (range) | 11.2 (1.1+, 18+) | 7.8 (2.1+, 16.4+)

* Based on the stratified Cox proportional hazard model.

†Based on stratified log-rank test.

‡Response: Best objective response as confirmed complete response or partial response.

§Based on Miettinen and Nurminen method stratified by PD-L1 status, platinum chemotherapy and smoking status.

NR = not reached

At the protocol specified final OS analysis, the median in the pemetrexed in combination with pembrolizumab and platinum chemotherapy arm was 22.0 months (95% CI: 19.5, 24.5) compared to 10.6 months (95% CI: 8.7, 13.6) in the placebo with pemetrexed and platinum chemotherapy arm, with an HR of 0.56 (95% CI: 0.46, 0.69).

Figure 1: Kaplan-Meier Curve for Overall Survival in KEYNOTE-189*

*Based on the protocol-specified final OS analysis

Initial Treatment in Combination with Cisplatin

The efficacy of pemetrexed was evaluated in Study JMDB (NCT00087711), a multi-center, randomized (1:1), open-label study conducted in 1725 chemotherapy-naive patients with Stage IIIb/IV NSCLC. Patients were randomized to receive pemetrexed with cisplatin or gemcitabine with cisplatin. Randomization was stratified by Eastern Cooperative Oncology Group Performance Status (ECOG PS 0 versus 1), gender, disease stage, basis for pathological diagnosis (histopathological/cytopathological), history of brain metastases, and investigative center. Pemetrexed was administered intravenously over 10 minutes at a dose of 500 mg/m^2 on Day 1 of each 21-day cycle. Cisplatin was administered intravenously at a dose of 75 mg/m^2 approximately 30 minutes after pemetrexed administration on Day 1 of each cycle, gemcitabine was administered at a dose of 1250 mg/m^2 on Day 1 and Day 8, and cisplatin was administered intravenously at a dose of 75 mg/m^2 approximately 30 minutes after administration of gemcitabine, on Day 1 of each 21-day cycle. Treatment was administered up to a total of 6 cycles; patients in both arms received folic acid, vitamin B12, and dexamethasone [see Dosage and Administration (2.4)]. The primary efficacy outcome measure was overall survival.

A total of 1725 patients were enrolled with 862 patients randomized to pemetrexed in combination with cisplatin and 863 patients to gemcitabine in combination with cisplatin. The median age was 61 years (range 26 to 83 years), 70% were male, 78% were White, 17% were Asian, 2.9% were Hispanic or Latino, and 2.1% were Black or African American, and <1% were other ethnicities. Among patients for whom ECOG PS (n=1722) and smoking history (n=1516) were collected, 65% had an ECOG PS of 1, 36% had an ECOG PS of 0, and 84% were smokers. For tumor characteristics, 73% had non-squamous NSCLC and 27% had squamous NSCLC; 76% had Stage IV disease. Among 1252 patients with non-squamous NSCLC histology, 68% had a diagnosis of adenocarcinoma, 12% had large cell histology and 20% had other histologic subtypes.

Efficacy results in Study JMDB are presented in Table 11 and Figure 2.

Table 11: Efficacy Results in Study JMDB

Efficacy Parameter | Pemetrexed plus Cisplatin (N=862) | Gemcitabine plus Cisplatin (N=863)
Overall Survival
Median (months) (95% CI) | 10.3 (9.8-11.2) | 10.3 (9.6-10.9)
Hazard ratio (HR)*,† (95% CI) | 0.94 (0.84-1.05)
Progression-Free Survival
Median (months) (95% CI) | 4.8 (4.6-5.3) | 5.1 (4.6-5.5)
Hazard ratio (HR)*,† (95% CI) | 1.04 (0.94-1.15)
Overall Response Rate (95% CI) | 27.1% (24.2-30.1) | 24.7% (21.8-27.6)
*Unadjusted for multiple comparisons.

†Adjusted for gender, stage, basis of diagnosis, and performance status.

Figure 2: Kaplan-Meier Curves for Overall Survival in Study JMDB

In pre-specified analyses assessing the impact of NSCLC histology on overall survival, clinically relevant differences in survival according to histology were observed. These subgroup analyses are shown in Table 12andFigures 3and4. This difference in treatment effect for pemetrexed based on histology demonstrating a lack of efficacy in squamous cell histology was also observed in Studies JMEN and JMEI.

Table 12: Overall Survival in NSCLC Histologic Subgroups in Study JMDB
Histologic Subgroups | Pemetrexed plus Cisplatin (N=862) | Gemcitabine plus Cisplatin (N=863)
Non-squamous NSCLC (N=1252)
Median (months) (95% CI) | 11.0 (10.1-12.5) | 10.1 (9.3-10.9)
HR*,† (95% CI) | 0.84 (0.74-0.96)
Adenocarcinoma (N=847)
Median (months) (95% CI) | 12.6 (10.7-13.6) | 10.9 (10.2-11.9)
HR*,† (95% CI) | 0.84 (0.71-0.99)
Large Cell (N=153)
Median (months) (95% CI) | 10.4 (8.6-14.1) | 6.7 (5.5-9.0)
HR*,† (95% CI) | 0.67 (0.48-0.96)
Non-squamous, not otherwise specified (N=252)
Median (months) (95% CI) | 8.6 (6.8-10.2) | 9.2 (8.1-10.6)
HR*,† (95% CI) | 1.08 (0.81-1.45)
Squamous Cell (N=473)
Median (months) (95% CI) | 9.4 (8.4-10.2) | 10.8 (9.5-12.1)
HR*,† (95% CI) | 1.23 (1.00-1.51)
*Unadjusted for multiple comparisons.
†Adjusted for ECOG PS, gender, disease stage, and basis for pathological diagnosis (histopathological/cytopathological).

Figure 3: Kaplan-Meier Curves for Overall Survival in Non-squamous NSCLC in Study JMDB

Figure 4: Kaplan-Meier Curves for Overall Survival in Squamous NSCLC in Study JMDB

Maintenance Treatment Following First-line Non-Pemetrexed Containing Platinum-Based Chemotherapy

The efficacy of pemetrexed as maintenance therapy following first-line platinum-based chemotherapy was evaluated in Study JMEN (NCT00102804), a multicenter, randomized (2:1), double-blind, placebo-controlled study conducted in 663 patients with Stage IIIb/IV NSCLC who did not progress after four cycles of platinum-based chemotherapy. Patients were randomized to receive pemetrexed 500 mg/m^2 intravenously every 21 days or placebo until disease progression or intolerable toxicity. Patients in both study arms received folic acid, vitamin B12, and dexamethasone [see Dosage and Administration (2.4)]. Randomization was carried out using a minimization approach [Pocock and Simon (1975)] using the following factors: gender, ECOG PS (0 versus 1), response to prior chemotherapy (complete or partial response versus stable disease), history of brain metastases (yes versus no), non-platinum component of induction therapy (docetaxel versus gemcitabine versus paclitaxel), and disease stage (IIIb versus IV). The major efficacy outcome measures were progression-free survival based on assessment by independent review and overall survival; both were measured from the date of randomization in Study JMEN.

A total of 663 patients were enrolled with 441 patients randomized to pemetrexed and 222 patients randomized to placebo. The median age was 61 years (range 26 to 83 years); 73% were male; 65% were White, 32% were Asian, 2.9% were Hispanic or Latino, and <2% were other ethnicities; 60% had an ECOG PS of 1; and 73% were current or former smokers. Median time from initiation of platinum-based chemotherapy to randomization was 3.3 months (range 1.6 to 5.1 months) and 49% of the population achieved a partial or complete response to first-line, platinum-based chemotherapy. With regard to tumor characteristics, 81% had Stage IV disease, 73% had non-squamous NSCLC and 27% had squamous NSCLC. Among the 481 patients with non-squamous NSCLC, 68% had adenocarcinoma, 4% had large cell, and 28% had other histologies.

Efficacy results are presented in Table 13andFigure 5.

Table 13: Efficacy Results in Study JMEN
Efficacy Parameter | Pemetrexed | Placebo
Overall survival | N=441 | N=222
Median (months) (95% CI) | 13.4 (11.9-15.9) | 10.6 (8.7-12.0)
Hazard ratio* (95% CI) | 0.79 (0.65-0.95)
p-value | p=0.012
Progression-free survival per independent review | N=387 | N=194
Median (months) (95% CI) | 4.0 (3.1-4.4) | 2.0 (1.5-2.8)
Hazard ratio* (95% CI) | 0.60 (0.49-0.73)
p-value | p<0.00001

*Hazard ratios are not adjusted for multiplicity but not for stratification variables.

The results of pre-specified subgroup analyses by NSCLC histology are presented in Table 14andFigures 6and7.

Efficacy Parameter | Overall Survival |  | Progression-Free Survival Per Independent Review
Efficacy Parameter | Pemetrexed (N=441) | Placebo (N=222) | Pemetrexed (N=387) | Placebo (N=194)
Non-squamous NSCLC (n=481)
Median (months) | 15.5 | 10.3 | 4.4 | 1.8
HR* (95% CI) | 0.70 (0.56-0.88) |  | 0.47 (0.37-0.60)
Adenocarcinoma (n=328)
Median (months) | 16.8 | 11.5 | 4.6 | 2.7
HR* (95% CI) | 0.73 (0.56-0.96) |  | 0.51 (0.38-0.68)
Large cell carcinoma (n=20)
Median (months) | 8.4 | 7.9 | 4.5 | 1.5
HR* (95% CI) | 0.98 (0.36-2.65) |  | 0.40 (0.12-1.29)
Other† (n=133)
Median (months) | 11.3 | 7.7 | 4.1 | 1.6
HR* (95% CI) | 0.61 (0.40-0.94) |  | 0.44 (0.28-0.68)
Squamous cell NSCLC (n=182)
Median (months) | 9.9 | 10.8 | 2.4 | 2.5
HR* (95% CI) | 1.07 (0.77-1.50) |  | 1.03 (0.71-1.49)
*Hazard ratios are not adjusted for multiplicity.
†Primary diagnosis of NSCLC not specified as adenocarcinoma, large cell carcinoma, or squamous cell carcinoma.

Figure 7: Kaplan-Meier Curves for Overall Survival in Squamous NSCLC in Study JMEN

Maintenance Treatment Following First-line Pemetrexed Plus Platinum Chemotherapy

The efficacy of pemetrexed as maintenance therapy following first-line platinum-based chemotherapy was also evaluated in PARAMOUNT (NCT00789373), a multi-center, randomized (2:1), double-blind, placebo-controlled study conducted in patients with Stage IIIb/IV non-squamous NSCLC who had completed four cycles of pemetrexed in combination with cisplatin and achieved a complete response (CR) or partial response (PR) or stable disease (SD). Patients were required to have an ECOG PS of 0 or 1. Patients were randomized to receive pemetrexed 500 mg/m^2 intravenously every 21 days or placebo until disease progression. Randomization was stratified by response to pemetrexed in combination with cisplatin induction therapy (CR or PR versus SD), disease stage (IIIb versus IV), and ECOG PS (0 versus 1). Patients in both arms received folic acid, vitamin B12, and dexamethasone. The main efficacy outcome measure was investigator-assessed progression-free survival (PFS) and an additional efficacy outcome measure was overall survival (OS); PFS and OS were measured from the time of randomization.

A total of 539 patients were enrolled with 359 patients randomized to pemetrexed and 180 patients randomized to placebo. The median age was 61 years (range 32 to 83 years); 58% were male; 95% were White, 4.5% were Asian, and <1% were Black or African American; 67% had an ECOG PS of 1; 78% were current or former smokers; and 43% of the population achieved a partial or complete response to first-line, platinum-based chemotherapy. With regard to tumor characteristics, 91% had Stage IV disease, 87% had adenocarcinoma, 7% had large cell, and 6% had other histologies.

Efficacy results for PARAMOUNT are presented in Table 15andFigure 8.

Efficacy Parameter | Pemetrexed (N=359) | Placebo (N=180)
Overall survival
Median (months) (95% CI) | 13.9 (12.8-16.0) | 11.0; (10.0-12.5)
Hazard ratio (HR)* (95% CI) | 0.78 (0.64-0.96)
p-value | p=0.02
Progression-free survival†
Median (months) (95% CI) | 4.1 (3.2-4.6) | 2.8 (2.6-3.1)
Hazard ratio (HR)* (95% CI) | 0.62 (0.49-0.79)
p-value | p<0.0001
*Hazard ratios are adjusted for multiplicity but not for stratification variables.
†Based on investigator’s assessment.

Figure 8: Kaplan-Meier Curves for Overall Survival in PARAMOUNT

Treatment of Recurrent Disease After Prior Chemotherapy

The efficacy of pemetrexed was evaluated in Study JMEI (NCT00004881), a multicenter, randomized (1:1), open-label study conducted in patients with Stage III or IV NSCLC that had recurred or progressed following one prior chemotherapy regimen for advanced disease. Patients were randomized to receive pemetrexed 500 mg/m^2 intravenously or docetaxel 75 mg/m^2 as a 1-hour intravenous infusion once every 21 days. Patients randomized to pemetrexed also received folic acid and vitamin B12. The study was designed to show that overall survival with pemetrexed was non-inferior to docetaxel, as the major efficacy outcome measure, and that overall survival was superior for patients randomized to pemetrexed compared to docetaxel, as a secondary outcome measure.

A total of 571 patients were enrolled with 283 patients randomized to pemetrexed and 288 patients randomized to docetaxel. The median age was 58 years (range 22 to 87 years); 72% were male; 71% were White, 24% were Asian, 2.8% were Black or African American, 1.8% were Hispanic or Latino, and <2% were other ethnicities; 88% had an ECOG PS of 0 or 1. With regard to tumor characteristics, 75% had Stage IV disease; 53% had adenocarcinoma, 30% had squamous histology; 8% large cell; and 9% had other histologic subtypes of NSCLC.

The efficacy results in the overall population and in subgroup analyses based on histologic subtype are provided in Tables 16 and 17, respectively. Study JMEI did not show an improvement in overall survival in the intent-to-treat population. In subgroup analyses, there was no evidence of a treatment effect on survival in patients with squamous NSCLC; the absence of a treatment effect in patients with NSCLC of squamous histology was also observed Studies JMDB and JMEN [see Clinical Studies (14.1)].

Efficacy Parameter | Pemetrexed (N=283) | Docetaxel (N=288)
Overall survival
Median (months) (95% CI) | 8.3 (7.0-9.4) | 7.9 (6.3-9.2)
Hazard ratio* (95% CI) | 0.99 (0.82-1.20)
Progression-free survival
Median (months) (95% CI) | 2.9 (2.4-3.1) | 2.9 (2.7-3.4)
Hazard ratio* (95% CI) | 0.97 (0.82-1.16)
Overall response rate (95% CI) | 8.5% (5.2-11.7) | 8.3% (5.1-11.5)
*Hazard ratios are not adjusted for multiplicity or for stratification variables.

Table 17: Exploratory Efficacy Analyses by Histologic Subgroup in Study JMEI

Histologic Subgroups | Pemetrexed (N=283) | Docetaxel (N=288)
Non-squamous NSCLC (N=399)
Median (months) (95% CI) | 9.3 (7.8-9.7) | 8.0 (6.3-9.3)
HR* (95% CI) | 0.89 (0.71-1.13)
Adenocarcinoma (N=301)
Median (months) (95% CI) | 9.0 (7.6-9.6) | 9.2 (7.5-11.3)
HR* (95% CI) | 1.09 (0.83-1.44)
Large Cell (N=47)
Median (months) (95% CI) | 12.8 (5.8-14.0) | 4.5 (2.3-9.1)
HR* (95% CI) | 0.38 (0.18-0.78)
Other† (N=51)
Median (months) (95% CI) | 9.4 (6.0-10.1) | 7.9 (4.0-8.9)
HR* (95% CI) | 0.62 (0.32-1.23)
Squamous NSCLC (N=172)
Median (months) (95% CI) | 6.2 (4.9-8.0) | 7.4 (5.6-9.5)
HR* (95% CI) | 1.32 (0.93-1.86)
*Hazard ratio unadjusted for multiple comparisons.
†Primary diagnosis of NSCLC not specified as adenocarcinoma, large cell carcinoma, or squamous cell carcinoma

14.2 Mesothelioma

The efficacy of pemetrexed was evaluated in Study JMCH (NCT00005636), a multicenter, randomized (1:1), single-blind study conducted in patients with MPM who had received no prior chemotherapy. Patients were randomized (n=456) to receive pemetrexed 500 mg/m^2 intravenously over 10 minutes followed 30 minutes later by cisplatin 75 mg/m^2 intravenously over two hours on Day 1 of each 21-day cycle or to receive cisplatin 75 mg/m^2 intravenously over 2 hours on Day 1 of each 21-day cycle; treatment continued until disease progression or intolerable toxicity. The study was modified after randomization and treatment of 117 patients to require that all patients receive folic acid 350 mcg to 1000 mcg daily beginning 1 to 3 weeks prior to the first dose of pemetrexed and continuing until 1 to 3 weeks after the last dose, vitamin B12 1000 mcg intramuscularly 1 to 3 weeks prior to first dose of pemetrexed and every 9 weeks thereafter, and dexamethasone 4 mg orally, twice daily, for 3 days starting the day prior to each pemetrexed dose. Randomization was stratified by multiple baseline variables including KPS, histologic subtype (epithelial, mixed, sarcomatoid, other), and gender. The major efficacy outcome measure was overall survival and additional efficacy outcome measures were time to disease progression, overall response rate, and response duration.

A total of 448 patients received at least one dose of protocol-specified therapy; 226 patients were randomized to and received at least one dose of pemetrexed plus cisplatin, and 222 patients were randomized to and received cisplatin. Among the 226 patients who received cisplatin with pemetrexed, 74% received full supplementation with folic acid and vitamin B12 during study therapy, 14% were never supplemented, and 12% were partially supplemented. Across the study population, the median age was 61 years (range: 20 to 86 years); 81% were male; 92% were White, 5% were Hispanic or Latino, 3.1% were Asian, and <1% were other ethnicities; and 54% had a baseline KPS score of 90 to 100% and 46% had a KPS score of 70 to 80%. With regard to tumor characteristics, 46% had Stage IV disease, 31% Stage III, 15% Stage II, and 7% Stage I disease at baseline; the histologic subtype of mesothelioma was epithelial in 68% of patients, mixed in 16%, sarcomatoid in 10% and other histologic subtypes in 6%. The baseline demographics and tumor characteristics of the subgroup of fully supplemented patients was similar to the overall study population.

The efficacy results from Study JMCH are summarized in Table 18andFigure 9.

Table 18: Efficacy Results in Study JMCH

Efficacy Parameter | All Randomized and Treated Patients (N=448) |  | Fully Supplemented Patients (N=331)
Efficacy Parameter | Pemetrexed/Cisplatin (N=226) | Cisplatin (N=222) | Pemetrexed/Cisplatin (N=168) | Cisplatin (N=163)
Median overall survival (months) | 12.1 | 9.3 | 13.3 | 10.0
(95% CI) | (10.0-14.4) | (7.8-10.7) | (11.4-14.9) | (8.4-11.9)
Hazard ratio* | 0.77 |  | 0.75
Log rank p-value | 0.020 |  | NA†
*Hazard ratios are not adjusted for stratification variables.
†Not a pre-specified analysis.

Figure 9: Kaplan-Meier Curves for Overall Survival in Study JMCH

Based upon prospectively defined criteria (modified Southwest Oncology Group methodology) the objective tumor response rate for pemetrexed plus cisplatin was greater than the objective tumor response rate for cisplatin alone. There was also improvement in lung function (forced vital capacity) in the pemetrexed plus cisplatin arm compared to the control arm.

15 REFERENCES

1. “OSHA Hazardous Drugs.” OSHA. [https://www.osha.gov/hazardous-drugs]”

16 HOW SUPPLIED/STORAGE AND HANDLING

How Supplied

Pemetrexed Injection is supplied as a sterile single-dose vial containing clear colorless to yellow or green-yellow solution in a clear glass vial with a grey rubber closure, aluminum cap, and light blue flip-off cap

Strength/Fill volume | NDC number | Pack style
100 mg/4 mL | NDC 0781-3518-76 | Carton containing one (1) single-dose vial
500 mg/20 mL | NDC 0781-3519-90 | Carton containing one (1) single-dose vial
1,000 mg/40 mL | NDC 0781-3520-91 | Carton containing one (1) single-dose vial

Storage and Handling

Store solution at 25°C (77°F); excursions permitted to 15°C to 30°C (59°F to 86°F) [see USP Controlled Room Temperature].

Protect from light. Keep the vial in the carton box until the time of use.

Pemetrexed Injection is a hazardous drug. Follow applicable special handling and disposal procedures [see References (15)].^1

17 PATIENT COUNSELING INFORMATION

Advise the patient to read the FDA-approved patient labeling (Patient Information).

Premedication and Concomitant Medication: Instruct patients to take folic acid as directed and to keep appointments for vitamin B12 injections to reduce the risk of treatment-related toxicity. Instruct patients of the requirement to take corticosteroids to reduce the risks of treatment-related toxicity [see Dosage and Administration (2.4) and Warnings and Precautions (5.1)].

Myelosuppression: Inform patients of the risk of low blood cell counts and instruct them to immediately contact their physician for signs of infection, fever, bleeding, or symptoms of anemia [see Warnings and Precautions (5.1)].

Renal Failure: Inform patients of the risks of renal failure, which may be exacerbated in patients with dehydration arising from severe vomiting or diarrhea. Instruct patients to immediately contact their healthcare provider for a decrease in urine output [see Warnings and Precautions (5.2)].

Bullous and Exfoliative Skin Disorders: Inform patients of the risks of severe and exfoliative skin disorders. Instruct patients to immediately contact their healthcare provider for development of bullous lesions or exfoliation in the skin or mucous membranes [see Warnings and Precautions (5.3)].

Interstitial Pneumonitis: Inform patients of the risks of pneumonitis. Instruct patients to immediately contact their healthcare provider for development of dyspnea or persistent cough [see Warnings and Precautions (5.4)].

Radiation Recall: Inform patients who have received prior radiation of the risks of radiation recall. Instruct patients to immediately contact their healthcare provider for development of inflammation or blisters in an area that was previously irradiated [see Warnings and Precautions (5.5)].

Increased Risk of Toxicity with Ibuprofen in Patients with Renal Impairment: Advise patients with mild to moderate renal impairment of the risks associated with concomitant ibuprofen use and instruct them to avoid use of all ibuprofen containing products for 2 days before, the day of, and 2 days following administration of Pemetrexed Injection [see Dosage and Administration (2.5), Warnings and Precautions (5.6), and Drug Interactions (7)].

Embryo-Fetal Toxicity: Advise females of reproductive potential and males with female partners of reproductive potential of the potential risk to a fetus [see Warnings and Precautions (5.7) and Use in Specific Populations (8.1)]. Advise females of reproductive potential to use effective contraception during treatment with Pemetrexed Injection and for 6 months after the last dose. Advise females to inform their prescriber of a known or suspected pregnancy. Advise males with female partners of reproductive potential to use effective contraception during treatment with Pemetrexed Injection and for 3 months after the last dose [see Warnings and Precautions (5.7) and Use in Specific Populations (8.3)].

Lactation: Advise women not to breastfeed during treatment with Pemetrexed Injection and for 1 week after the last dose [see Use in Specific Populations (8.2)].

Manufactured by FAREVA Unterach GmbH for

Sandoz Inc., Princeton, NJ 08540

PATIENT INFORMATION
Pemetrexed (pem-e-TREX-ed) Injection

for intravenous use

What is Pemetrexed Injection?
Pemetrexed Injection is a prescription medicine used to treat:

- a kind of lung cancer called non-squamous non-small cell lung cancer (NSCLC). Pemetrexed Injection is used:
  - as the first treatment in combination with pembrolizumab and platinum chemotherapy when your lung cancer with no abnormal EGFR or ALK gene has spread (advanced NSCLC).
  - as the first treatment in combination with cisplatin when your lung cancer has spread (advanced NSCLC).
  - alone as maintenance treatment after you have received 4 cycles of chemotherapy that contains platinum for first treatment of your advanced NSCLC and your cancer has not progressed.
  - alone when your lung cancer has returned or spread after prior chemotherapy.
Pemetrexed Injection is not for use for the treatment of people with squamous cell non-small cell lung cancer.
- a kind of cancer called malignant pleural mesothelioma. This cancer affects the lining of the lungs and chest wall. Pemetrexed Injection is used in combination with cisplatin as the first treatment for malignant pleural mesothelioma that cannot be removed by surgery or you are not able to have surgery.

Pemetrexed Injection has not been shown to be safe and effective in children.

Do not take Pemetrexed Injection if you have had a severe allergic reaction to any medicine that contains pemetrexed.

Before taking Pemetrexed Injection, tell your healthcare provider about all of your medical conditions, including if you:

- have kidney problems.
- have had radiation therapy.
- are pregnant or plan to become pregnant. Pemetrexed Injection can harm your unborn baby.
Females who are able to become pregnant:
- Your healthcare provider will check to see if you are pregnant before you start treatment with Pemetrexed Injection.
- You should use effective birth control (contraception) during treatment with Pemetrexed Injection and for 6 months after the last dose. Tell your healthcare provider right away if you become pregnant or think you are pregnant during treatment with Pemetrexed Injection.
Males with female partners who are able to become pregnant should use effective birth control (contraception) during treatment with Pemetrexed Injection and for 3 months after the last dose.
- are breastfeeding or plan to breastfeed. It is not known if pemetrexed passes into breast milk. Do not breastfeed during treatment with Pemetrexed Injection and for 1 week after the last dose.

Tell your healthcare provider about all the medicines you take, including prescription and over-the-counter medicines, vitamins, and herbal supplements.

Tell your healthcare provider if you have kidney problems and take a medicine that contains ibuprofen. You should avoid taking ibuprofen for 2 days before, the day of, and 2 days after receiving treatment with Pemetrexed Injection.

How is Pemetrexed Injection given?

- It is very important to take folic acid and vitamin B12 during your treatment with Pemetrexed Injection to lower your risk of harmful side effects.
  - Take folic acid exactly as prescribed by your healthcare provider 1 time a day, beginning 7 days (1 week) before your first dose of Pemetrexed Injection and continue taking folic acid until 21 days (3 weeks) after your last dose of Pemetrexed Injection.
  - Your healthcare provider will give you vitamin B12 injections during treatment with Pemetrexed Injection. You will get your first vitamin B12 injection 7 days (1 week) before your first dose of Pemetrexed Injection, and then every 3 cycles.
- Your healthcare provider will prescribe a medicine called corticosteroid for you to take 2 times a day for 3 days, beginning the day before each treatment with Pemetrexed Injection.
- Pemetrexed Injection is given to you by intravenous (IV) infusion into your vein. The infusion is given over 10 minutes.
- Pemetrexed Injection is usually given once every 21 days (3 weeks).

What are the possible side effects of Pemetrexed Injection?
Pemetrexed Injection can cause serious side effects, including:

- Low blood cell counts. Low blood cell counts can be severe, including low white blood cell counts (neutropenia), low platelet counts (thrombocytopenia), and low red blood cell counts (anemia). Your healthcare provider will do blood tests to check your blood cell counts regularly during your treatment with Pemetrexed Injection. Tell your healthcare provider right away if you have any signs of infection, fever, bleeding, or severe tiredness during your treatment with Pemetrexed Injection.
- Kidney problems, including kidney failure. Pemetrexed Injection can cause severe kidney problems that can lead to death. Severe vomiting or diarrhea can lead to loss of fluids (dehydration) which may cause kidney problems to become worse. Tell your healthcare provider right away if you have a decrease in the amount of urine you make.
- Severe skin reactions. Severe skin reactions that may lead to death can happen with Pemetrexed Injection. Tell your healthcare provider right away if you develop blisters, skin sores, skin peeling, or painful sores, or ulcers in your mouth, nose, throat or genital area.
- Lung problems (pneumonitis). Pemetrexed Injection can cause serious lung problems that can lead to death. Tell your healthcare provider right away if you get any new or worsening symptoms of shortness of breath, cough, or fever.
- Radiation recall. Radiation recall is a skin reaction that can happen in people who have received radiation treatment in the past and are treated with Pemetrexed Injection. Tell your healthcare provider if you get swelling, blistering, or a rash that looks like a sunburn in an area that was previously treated with radiation.

The most common side effects of Pemetrexed Injection when given alone are:

- tiredness

- nausea

- loss of appetite

The most common side effects of Pemetrexed Injection when given with cisplatin are:

- vomiting
- swelling or sores in your mouth or sore throat
- constipation

- low white blood cell counts (neutropenia)
- low platelet counts (thrombocytopenia)
- low red blood cell counts (anemia)

The most common side effects of Pemetrexed Injection when given with pembrolizumab and platinum chemotherapy are:

- tiredness and weakness
- constipation
- vomiting
- diarrhea
- loss of appetite

- nausea
- rash
- shortness of breath
- cough
- fever

Pemetrexed Injection may cause fertility problems in males. This may affect your ability to father a child. It is not known if these effects are reversible. Talk to your healthcare provider if this is a concern for you.

Your healthcare provider will do blood tests to check for side effects during treatment with Pemetrexed Injection. Your healthcare provider may change your dose of Pemetrexed Injection, delay treatment, or stop treatment if you have certain side effects.

Tell your healthcare provider if you have any side effect that bothers you or that does not go away.
These are not all of the possible side effects of Pemetrexed Injection. For more information, ask your healthcare provider or pharmacist.
Call your doctor for medical advice about side effects. You may report side effects to FDA at 1-800-FDA-1088.

General information about the safe and effective use of Pemetrexed Injection.
Medicines are sometimes prescribed for purposes other than those listed in a Patient Information leaflet. You can ask your pharmacist or healthcare provider for information about Pemetrexed Injection that is written for health professionals.

What are the ingredients in Pemetrexed Injection?
Active ingredient: pemetrexed
Inactive ingredients:

sodium thiosulfate pentahydrate, propylene glycol, water for injection. Hydrochloric acid and/or sodium hydroxide may have been added to adjust pH.

Manufactured by FAREVA Unterach GmbH for

Sandoz Inc., Princeton, NJ 08540

For more information, call 1-800-525-8747.

This Patient Information has been approved by the U.S. Food and Drug Administration. Revised: December 2025

Principal Display Panel – 4 mL

NDC 0781-3518-76

Pemetrexed Injection

100 mg/4 mL

(25 mg/mL)

For Intravenous Infusion After Dilution

Warning: Hazardous Drug

Single-Dose Vial

Discard unused Portion

Rx Only

Sterile

SANDOZ

Principal Display Panel – 20 mL

NDC 0781-3519-90

Pemetrexed Injection

500 mg/20 mL

(25 mg/mL)

For Intravenous Infusion After Dilution

Warning: Hazardous Drug

Single-Dose Vial

Discard unused Portion.

Rx Only

Sterile

SANDOZ

Principal Display Panel

NDC 0781-3520-91

Pemetrexed Injection

1000 mg/40 mL

(25 mg/mL)

For Intravenous Infusion After Dilution

Warning: Hazardous Drug

Single-Dose Vial

Discard unused Portion.

Rx Only

Sterile

SANDOZ